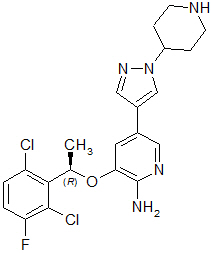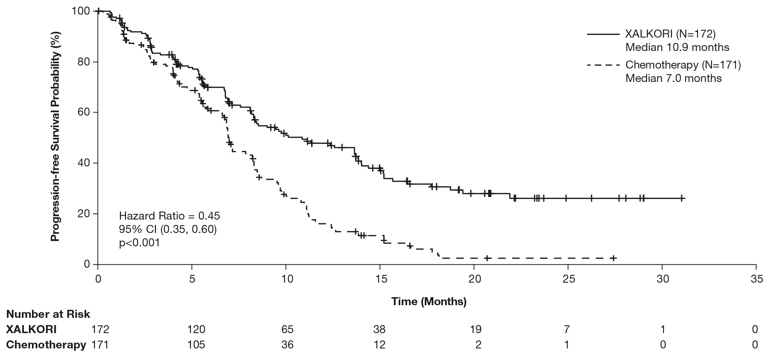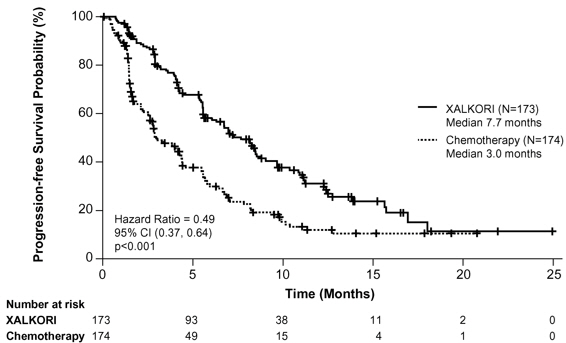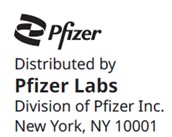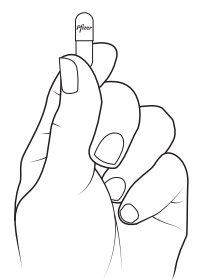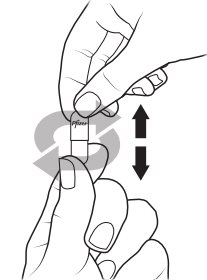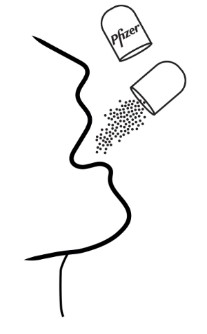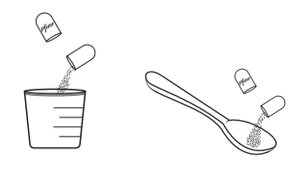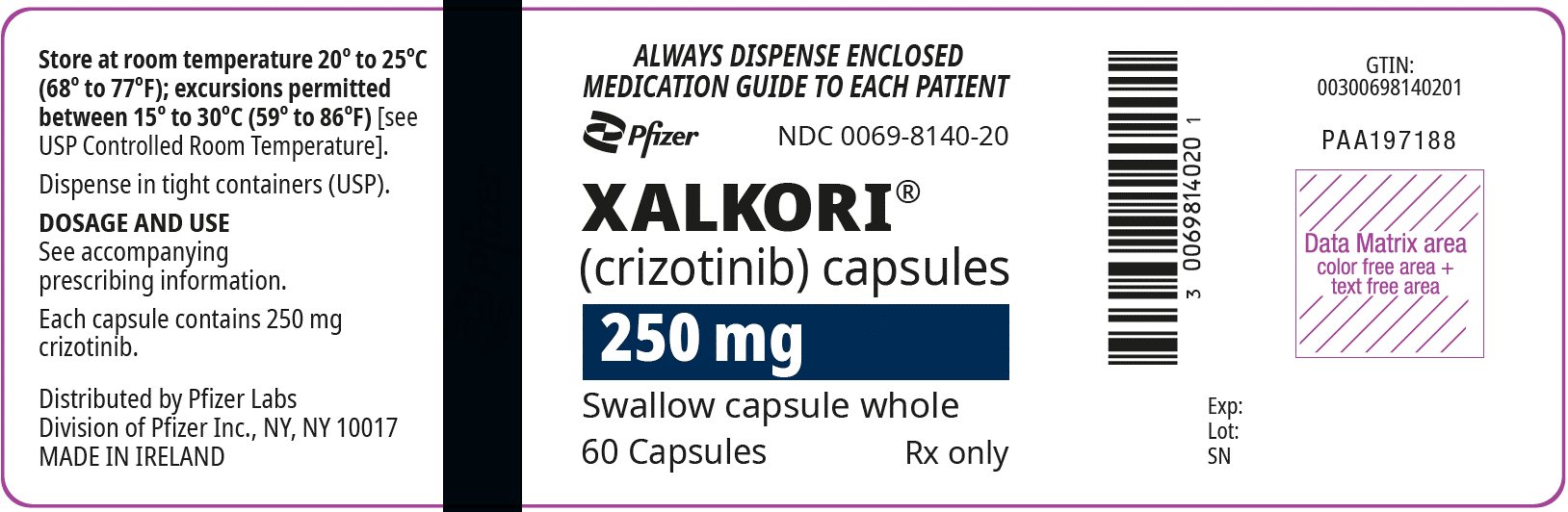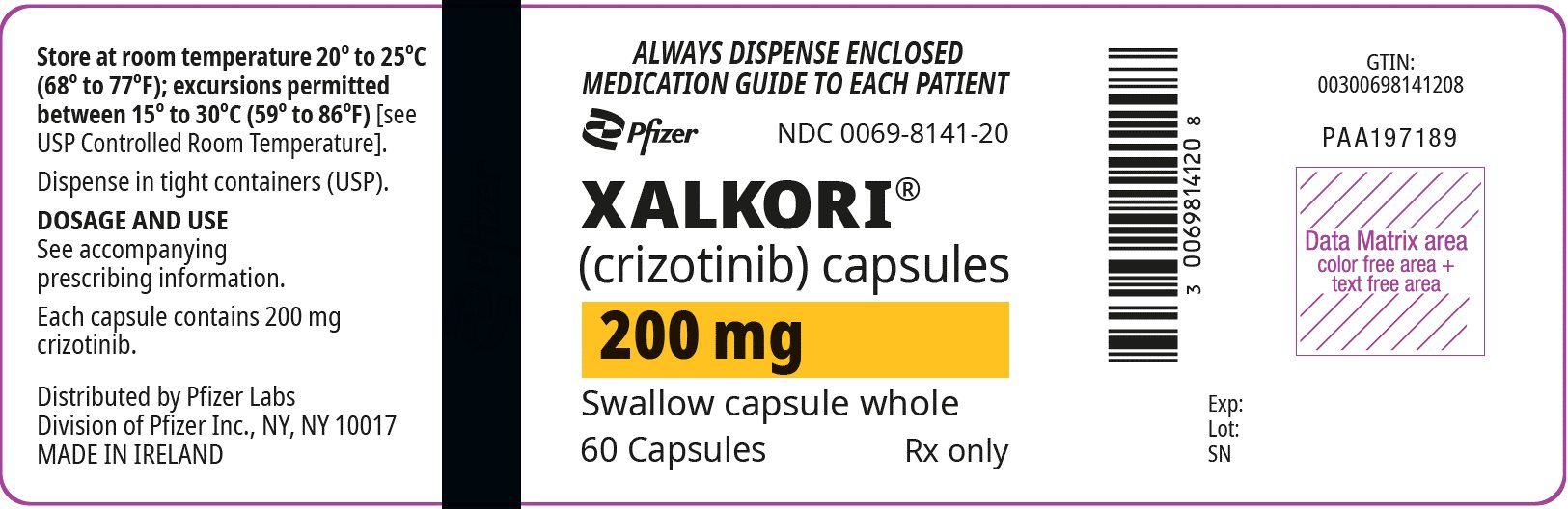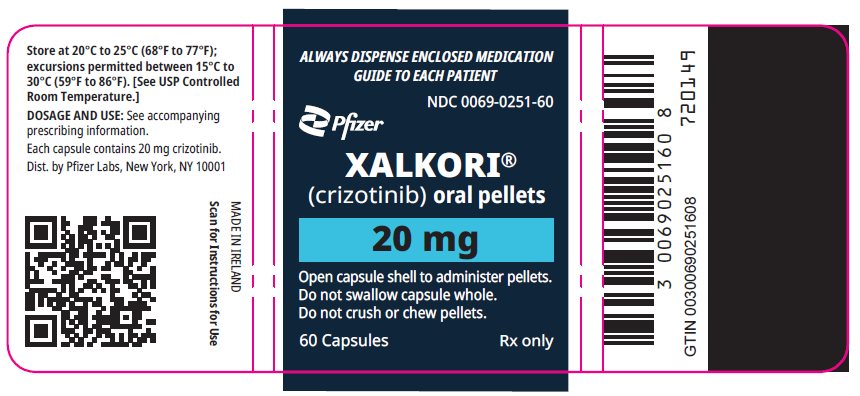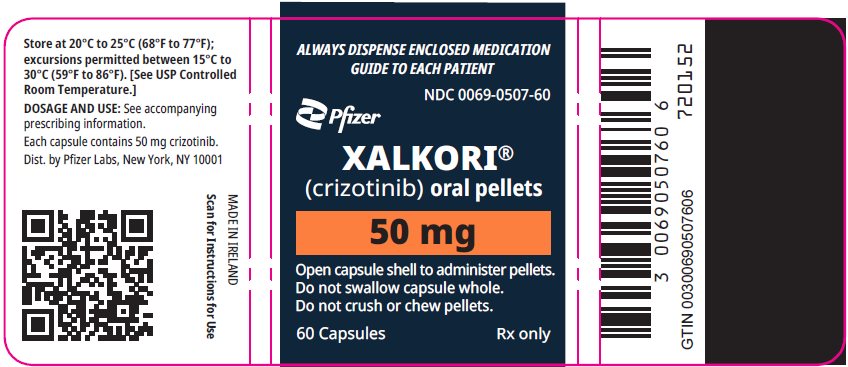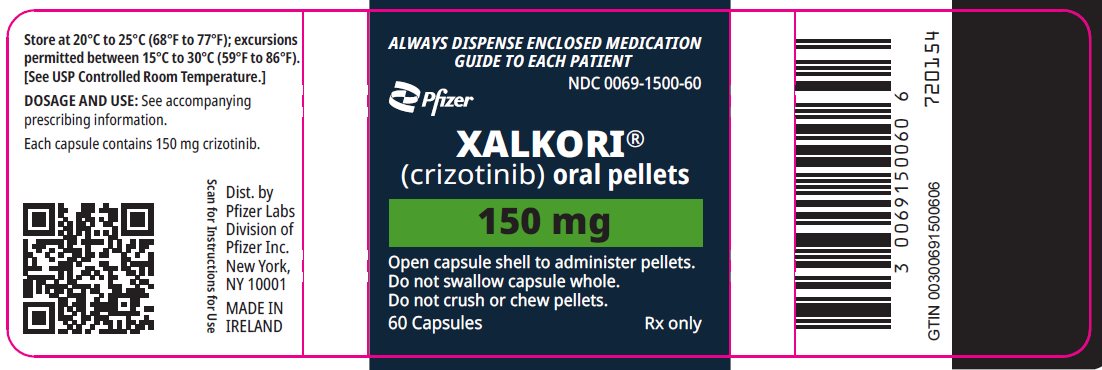 DRUG LABEL: Xalkori
NDC: 0069-8140 | Form: CAPSULE
Manufacturer: Pfizer Laboratories Div Pfizer Inc
Category: prescription | Type: HUMAN PRESCRIPTION DRUG LABEL
Date: 20250722

ACTIVE INGREDIENTS: CRIZOTINIB 250 mg/1 1
INACTIVE INGREDIENTS: SILICON DIOXIDE; MICROCRYSTALLINE CELLULOSE; ANHYDROUS DIBASIC CALCIUM PHOSPHATE; MAGNESIUM STEARATE; GELATIN, UNSPECIFIED; TITANIUM DIOXIDE; FERRIC OXIDE RED; SHELLAC; PROPYLENE GLYCOL; AMMONIA; POTASSIUM HYDROXIDE; FERROSOFERRIC OXIDE; SODIUM STARCH GLYCOLATE TYPE A

HIGHLIGHTS OF PRESCRIBING INFORMATION

These highlights do not include all the information needed to use XALKORI® safely and effectively. See full prescribing information for XALKORI.
XALKORI® (crizotinib) capsules, for oral use
XALKORI® (crizotinib) oral pellets
Initial U.S. Approval: 2011

RECENT MAJOR CHANGES

Dosage and Administration (2) | 9/2023

1 INDICATIONS AND USAGE

XALKORI is a kinase inhibitor indicated for the treatment of

- adult patients with metastatic non-small cell lung cancer (NSCLC) whose tumors are anaplastic lymphoma kinase (ALK) or ROS1-positive as detected by an FDA-approved test. (1.1, 2.1)
- pediatric patients 1 year of age and older and young adults with relapsed or refractory, systemic anaplastic large cell lymphoma (ALCL) that is ALK-positive. (1.2, 2.3)
  - Limitations of Use: The safety and efficacy of XALKORI have not been established in older adults with relapsed or refractory, systemic ALK-positive ALCL.
- adult and pediatric patients 1 year of age and older with unresectable, recurrent, or refractory inflammatory myofibroblastic tumor (IMT) that is ALK-positive. (1.3, 2.3)

2 DOSAGE AND ADMINISTRATION

- Metastatic NSCLC: The recommended dosage is 250 mg orally twice daily. (2.3)
- Systemic ALCL: The recommended dosage is 280 mg/m^2 orally twice daily based on body surface area. (2.3)
- Unresectable IMT:
  - Adult: The recommended dosage is 250 mg orally twice daily. (2.3)
  - Pediatric: The recommended dosage is 280 mg/m^2 orally twice daily based on body surface area. (2.3)
- See full prescribing information for dosage adjustments by indication for patients with moderate or severe hepatic impairment or severe renal impairment. (2.7, 2.8)

3 DOSAGE FORMS AND STRENGTHS

Capsules: 200 mg, 250 mg (3)

Oral pellets: 20 mg, 50 mg, 150 mg (3)

4 CONTRAINDICATIONS

None. (4)

5 WARNINGS AND PRECAUTIONS

- Hepatotoxicity: Fatal hepatotoxicity has occurred. Monitor with periodic liver testing. Temporarily suspend, dose reduce, or permanently discontinue XALKORI. (2.2, 2.6, 5.1)
- Interstitial Lung Disease (ILD)/Pneumonitis: Permanently discontinue in patients with ILD/pneumonitis. (2.6, 5.2)
- QT Interval Prolongation: Monitor electrocardiograms and electrolytes in patients who have a history of or predisposition for QTc prolongation, or who are taking medications that prolong QT. Temporarily suspend, dose reduce, or permanently discontinue XALKORI. (2.6, 5.3)
- Bradycardia: XALKORI can cause bradycardia. Monitor heart rate and blood pressure regularly. Temporarily suspend, dose reduce, or permanently discontinue XALKORI. (2.6, 5.4)
- Severe Visual Loss: XALKORI can cause visual changes including severe visual loss. Monitor and evaluate for ocular toxicity throughout treatment. Discontinue XALKORI in patients with severe visual loss. (2.2, 2.6, 5.5)
- Gastrointestinal Toxicity in Pediatric and Young Adult Patients with ALCL or Pediatric Patients with IMT: XALKORI can cause severe nausea, vomiting, diarrhea, and stomatitis. Provide standard antiemetic and antidiarrheal agents. Temporarily suspend, dose reduce, or permanently discontinue XALKORI. (2.6, 5.6)
- Embryo-Fetal Toxicity: Can cause fetal harm. Advise females of reproductive potential of the potential risk to a fetus and use of effective contraception. (5.7, 8.1, 8.3)

6 ADVERSE REACTIONS

The most common adverse reactions (≥25%) in adult patients with NSCLC are vision disorders, nausea, diarrhea, vomiting, edema, constipation, elevated transaminases, fatigue, decreased appetite, upper respiratory infection, dizziness, and neuropathy. (6.1)
The most common adverse reactions (≥35%) in patients with ALCL are diarrhea, vomiting, nausea, vision disorder, headache, musculoskeletal pain, stomatitis, fatigue, decreased appetite, pyrexia, abdominal pain, cough, and pruritus. Grade 3–4 laboratory abnormalities (≥15%) are neutropenia, lymphopenia, and thrombocytopenia. (6.1)
The most common adverse reactions (≥35%) in adult patients with IMT are vision disorders, nausea, and edema. (6.1)
The most common adverse reactions (≥35%) in pediatric patients with IMT are vomiting, nausea, diarrhea, abdominal pain, rash, vision disorder, upper respiratory tract infection, cough, pyrexia, musculoskeletal pain, fatigue, edema, constipation, and headache. (6.1)

To report SUSPECTED ADVERSE REACTIONS, contact Pfizer Inc. at 1-800-438-1985 or FDA at 1-800-FDA-1088 or www.fda.gov/medwatch.

7 DRUG INTERACTIONS

- Strong CYP3A Inhibitors: Avoid concomitant use. (2.9, 7.1)
- Strong CYP3A Inducers: Avoid concomitant use. (7.1)
- CYP3A Substrates: Avoid concomitant use with CYP3A substrates, where minimal concentration changes may lead to serious adverse reactions. (7.2)

8 USE IN SPECIFIC POPULATIONS

Lactation: Advise not to breastfeed. (8.2)

FULL PRESCRIBING INFORMATION

1 INDICATIONS AND USAGE

1.1 ALK- or ROS1-Positive Metastatic Non-Small Cell Lung Cancer

XALKORI is indicated for the treatment of adult patients with metastatic non-small cell lung cancer (NSCLC) whose tumors are anaplastic lymphoma kinase (ALK) or ROS1-positive as detected by an FDA-approved test [see Dosage and Administration (2.1)].

1.2 Relapsed or Refractory, Systemic ALK-Positive Anaplastic Large Cell Lymphoma

XALKORI is indicated for the treatment of pediatric patients 1 year of age and older and young adults with relapsed or refractory, systemic anaplastic large cell lymphoma (ALCL) that is ALK-positive.

Limitations of Use: The safety and efficacy of XALKORI have not been established in older adults with relapsed or refractory, systemic ALK-positive ALCL.

1.3 Unresectable, Recurrent, or Refractory ALK-Positive Inflammatory Myofibroblastic Tumor

XALKORI is indicated for the treatment of adult and pediatric patients 1 year of age and older with unresectable, recurrent, or refractory inflammatory myofibroblastic tumor (IMT) that is ALK-positive.

2 DOSAGE AND ADMINISTRATION

2.1 Patient Selection

Select patients for the treatment of metastatic NSCLC with XALKORI based on the presence of ALK or ROS1 positivity in tumor specimens [see Clinical Studies (14.1, 14.2, 14.3)].

Information on FDA-approved tests for the detection of ALK and ROS1 rearrangements in NSCLC is available at http://www.fda.gov/companiondiagnostics.

2.2 Recommended Testing During Treatment with XALKORI

- Monitor liver function tests, including alanine aminotransferase (ALT), aspartate aminotransferase (AST), and total bilirubin, every 2 weeks during the first 2 months of treatment, then once a month, and as clinically indicated, with more frequent repeat testing for increased liver transaminases, alkaline phosphatase, or total bilirubin in patients who develop increased transaminases [see Warnings and Precautions (5.1)].
- Monitor complete blood counts including differential weekly for the first month of therapy and then at least monthly, with more frequent monitoring if Grade 3 or 4 abnormalities, fever, or infection occur [see Adverse Reactions (6.1)].
- For pediatric and young adult patients with ALCL or pediatric patients with IMT, obtain baseline and follow-up ophthalmologic examinations including retinal examination within 1 month of starting XALKORI and every 3 months thereafter [see Warnings and Precautions (5.5)].

2.3 Recommended Dosage

The recommended dosage of XALKORI is provided in Table 1.

Table 1. Recommended Dosage of XALKORI
Indication | Recommended Dosage of XALKORI
ALK- or ROS1-Positive Metastatic NSCLC | Adults: 250 mg orally twice daily
Relapsed or Refractory, Systemic ALK-Positive ALCL | Pediatric Patients and Young Adults: 280 mg/m^2 orally twice daily [See Table 2 for Recommended Dosage based on body surface area for pediatric patients and young adults with ALCL for the capsules and oral pellets.]
Unresectable, Recurrent, or Refractory ALK-Positive IMT | Adults: 250 mg orally twice daily
Unresectable, Recurrent, or Refractory ALK-Positive IMT | Pediatric Patients: 280 mg/m^2 orally twice daily [See Table 3 for Recommended Dosage based on body surface area for pediatric patients with IMT for the capsules and oral pellets.]

Recommended Dosage for Adult Patients with ALK- or ROS1-Positive Metastatic NSCLC

- The recommended dosage for adult patients with ALK- or ROS1-positive metastatic NSCLC is XALKORI capsules 250 mg orally, twice daily, with or without food until disease progression or unacceptable toxicity occurs.
- For adults who cannot swallow capsules, the recommended dosage of XALKORI pellets is 250 mg (2 x 50 mg + 1 x 150 mg) orally, twice daily, with or without food until disease progression or unacceptable toxicity occurs.

Recommended Dosage for Pediatric and Young Adult Patients with ALK-Positive ALCL

- The recommended dosage for pediatric patients 1 year of age and older and young adults with relapsed or refractory, systemic ALK-positive ALCL is based on body surface area (BSA) and is provided in Table 2.
- Administer XALKORI capsules or pellets orally, twice daily, with or without food until disease progression or unacceptable toxicity occurs.

Table 2 provides the dosage based on body surface area (BSA) for XALKORI capsules or pellets.

Table 2. Recommended XALKORI Dosage for Pediatric Patients 1 Year of Age and Older and Young Adults With ALK-Positive ALCL Using Either XALKORI Capsules or Pellets
Body Surface Area (BSA) | Recommended XALKORI Dosage to Achieve 280 mg/m^2; Twice Daily | Dose Strength Combinations of XALKORI Pellets to Administer [No more than 4 oral pellet shells are to be used for a single dose.] | Dose Strength Combinations of XALKORI Capsules to Administer
0.38 to 0.46 m^2 | 120 mg twice daily | 1 x 20 mg + 2 x 50 mg | ---
0.47 to 0.51 m^2 | 140 mg twice daily | 2 x 20 mg + 2 x 50 mg | ---
0.52 to 0.61 m^2 | 150 mg twice daily | 1 x 150 mg | ---
0.62 to 0.80 m^2 | 200 mg twice daily | 1 x 50 mg + 1 x 150 mg | ---
0.81 to 0.97 m^2 | 250 mg twice daily | 2 x 50 mg + 1 x 150 mg | ---
0.98 to 1.16 m^2 | 300 mg twice daily | 2 x 150 mg | ---
1.17 to 1.33 m^2 | 350 mg twice daily | 1 x 50 mg + 2 x 150 mg | ---
1.34 to 1.51 m^2 | 400 mg twice daily | 2 x 50 mg + 2 x 150 mg | 2 x 200 mg
1.52 to 1.69 m^2 | 450 mg twice daily | 3 x 150 mg | 1 x 200 mg + 1 x 250 mg
1.7 m^2 or greater | 500 mg twice daily | 1 x 50 mg + 3 x 150 mg | 2 x 250 mg

Recommended Dosage for Pediatric and Adult Patients with ALK-Positive IMT

- The recommended dosage for adult patients with unresectable, recurrent, or refractory ALK-positive IMT is provided in Table 1.
- The recommended dosage for pediatric patients 1 year of age and older with unresectable, recurrent, or refractory ALK-positive IMT is based on BSA and is provided in Table 3.
- Administer XALKORI capsules or pellets orally twice daily, with or without food, until disease progression or unacceptable toxicity occurs.

Table 3 provides the dosage based on BSA for XALKORI capsules or pellets.

Table 3. Recommended XALKORI Dosage for Pediatric Patients 1 Year of Age and Older with ALK-positive IMT Using Either XALKORI Capsules or Pellets
Body Surface Area (BSA) | Recommended XALKORI Dosage to Achieve 280 mg/m^2; Twice Daily | Dose Strength Combinations of XALKORI Pellets to Administer [No more than 4 oral pellet shells are to be used for a single dose.] | Dose Strength Combinations of XALKORI Capsules to Administer
0.38 to 0.46 m^2 | 120 mg twice daily | 1 x 20 mg + 2 x 50 mg | ---
0.47 to 0.51 m^2 | 140 mg twice daily | 2 x 20 mg + 2 x 50 mg | ---
0.52 to 0.61 m^2 | 150 mg twice daily | 1 x 150 mg | ---
0.62 to 0.80 m^2 | 200 mg twice daily | 1 x 50 mg + 1 x 150 mg | ---
0.81 to 0.97 m^2 | 250 mg twice daily | 2 x 50 mg + 1 x 150 mg | ---
0.98 to 1.16 m^2 | 300 mg twice daily | 2 x 150 mg | ---
1.17 to 1.33 m^2 | 350 mg twice daily | 1 x 50 mg + 2 x 150 mg | ---
1.34 to 1.51 m^2 | 400 mg twice daily | 2 x 50 mg + 2 x 150 mg | 2 x 200 mg
1.52 to 1.69 m^2 | 450 mg twice daily | 3 x 150 mg | 1 x 200 mg + 1 x 250 mg
1.7 m^2 or greater | 500 mg twice daily | 1 x 50 mg + 3 x 150 mg | 2 x 250 mg

2.4 Administration

- Administer XALKORI capsules or pellets orally, twice daily, with or without food.
- If a dose of XALKORI capsules or pellets is missed, make up that dose unless the next dose is due within 6 hours.
- If vomiting occurs after taking a dose of XALKORI capsules or pellets, do not take an additional dose. Take the next dose at the regular scheduled time.

XALKORI Capsules

- Swallow XALKORI capsules whole, with or without food twice daily.
- Do not chew, crush or split XALKORI capsules.

XALKORI Pellets

- XALKORI pellets are supplied encapsulated in shells.
- Do not chew or crush XALKORI pellets.
- Do not swallow XALKORI pellets encapsulated in the shell.
- XALKORI pellets can be administered by 2 options:
1. Open shell(s) containing XALKORI pellets and empty the contents directly into the patient’s mouth.
2. Open shell(s) containing XALKORI pellets and empty the contents into a consumer-supplied oral dosing aid (e.g., spoon, medicine cup). Administer XALKORI pellets via the dosing aid directly into the patient’s mouth.
- Immediately after administration, give a sufficient amount of water to ensure that all medication is swallowed.

2.5 Concomitant Treatments for Pediatric and Young Adult Patients with ALCL or Pediatric Patients with IMT

Antiemetics are recommended prior to and during treatment with XALKORI to prevent nausea and vomiting. Provide standard antiemetic and antidiarrheal agents for gastrointestinal toxicities.

Consider intravenous or oral hydration for patients at risk of dehydration, and replace electrolytes as clinically indicated [see Warnings and Precautions (5.6)].

2.6 Dosage Modifications for Adverse Reactions

The recommended dosage modifications for adverse reactions for adult patients with NSCLC or IMT are provided in Table 4.

Table 4. Recommended Dosage Reductions for Adverse Reactions for Adult Patients with NSCLC or IMT Using XALKORI Capsules or Pellets
Dose Reduction | Dose and Schedule
First Dose Reduction | 200 mg twice daily
Second Dose Reduction | 250 mg once daily
Permanently discontinue XALKORI capsules or pellets if unable to tolerate 250 mg taken once daily.

The recommended dosage modifications for adverse reactions for pediatric patients with ALCL or IMT and young adults with ALCL are based on body surface area and are provided in Table 5.

Table 5. Recommended Dosage Reductions for Adverse Reactions for Pediatric Patients with ALCL or IMT and Young Adults with ALCL Using XALKORI Capsules or Pellets
Body Surface Area; (BSA) | First Dose Reduction |  | Second Dose Reduction [Permanently discontinue in patients who are unable to tolerate XALKORI capsules or pellets after 2 dose reductions.]
Body Surface Area; (BSA) | Dosage | Dosage Form and Strength to Achieve Recommended Dose Reduction | Dosage | Dosage Form and Strength to Achieve Recommended Dose Reduction
0.38 to 0.46 m^2 | 90 mg; twice daily | Pellets: 2 x 20 mg +; 1 x 50 mg | 70 mg; twice daily | Pellets: 1 x 20 mg +; 1 x 50 mg
0.47 to 0.51 m^2 | 100 mg; twice daily | Pellets: 2 x 50 mg | 80 mg; twice daily | Pellets: 4 x 20 mg
0.52 to 0.61 m^2 | 120 mg; twice daily | Pellets: 1 x 20 mg +; 2 x 50 mg | 90 mg; twice daily | Pellets: 2 x 20 mg +; 1 x 50 mg
0.62 to 0.80 m^2 | 150 mg; twice daily | Pellets: 1 x 150 mg | 120 mg; twice daily | Pellets: 1 x 20 mg +; 2 x 50 mg
0.81 to 0.97 m^2 | 200 mg; twice daily | Pellets: 1 x 50 mg +; 1 x 150 mg | 150 mg; twice daily | Pellets: 1 x 150 mg
0.98 to 1.16 m^2 | 220 mg; twice daily | Pellets: 1 x 20 mg +; 1 x 50 mg +; 1 x 150 mg | 170 mg; twice daily | Pellets: 1 x 20 mg +; 1 x 150 mg
1.17 to 1.33 m^2 | 250 mg; twice daily | Pellets: 2 x 50 mg +; 1 x 150 mg | 200 mg; twice daily | Pellets: 1 x 50 mg +; 1 x 150 mg
1.34 to 1.69 m^2 | 250 mg; twice daily | Pellets: 2 x 50 mg +; 1 x 150 mg; Or; Capsule: 1 x 250 mg | 200 mg; twice daily | Pellets: 1 x 50 mg +; 1 x 150 mg; Or; Capsule: 1 x 200 mg
1.7 m^2 or greater | 400 mg; twice daily | Pellets: 2 x 50 mg +; 2 x 150 mg; Or; Capsule: 2 x 200 mg | 250 mg; twice daily | Pellets: 2 x 50 mg +; 1 x 150 mg; Or; Capsule: 1 x 250 mg

Recommended Dosage Modifications for Hematologic Adverse Reactions for Adult Patients with NSCLC or IMT

The recommended dosage modifications for hematologic adverse reactions for adult patients with NSCLC or IMT are provided in Table 6.

Table 6. Adult Patients with NSCLC or IMT: XALKORI Dosage Modification – Hematologic Toxicities [Except lymphopenia (unless associated with clinical events, e.g., opportunistic infections).]
Severity of Adverse Reaction [Grade based on National Cancer Institute (NCI) Common Terminology Criteria for Adverse Events (CTCAE), version 4.0.] | XALKORI Dosage Modification
Grade 3 | Withhold until recovery to Grade 2 or less, then resume at the same dosage.
Grade 4 | Withhold until recovery to Grade 2 or less, then resume at next lower dosage.

Monitor complete blood counts including differential weekly for the first month of therapy and then at least monthly, with more frequent monitoring if Grade 3 or 4 abnormalities, fever, or infection occur.

Recommended Dosage Modifications for Hematologic Adverse Reactions in Pediatric and Young Adult Patients with ALCL or Pediatric Patients with IMT

The recommended dosage modifications for hematologic adverse reactions in pediatric and young adult patients with ALCL or pediatric patients with IMT are provided in Table 7.

Table 7. Pediatric and Young Adult Patients with ALCL or Pediatric Patients with IMT: XALKORI Dosage Modification for Hematologic Adverse Reactions
Severity of Adverse Reaction | XALKORI Dosage Modification
Absolute Neutrophil Count (ANC)
Less than 0.5 x 10^9/L | First occurrence: Withhold until recovery to ANC greater than 1.0 x 10^9/L, then resume at the next lower dosage. Second occurrence:; - Permanently discontinue for recurrence complicated by febrile neutropenia or infection. - For uncomplicated Grade 4 neutropenia, either permanently discontinue, or withhold until recovery to ANC greater than 1.0 x 10^9/L, then resume at the next lower dosage. [Permanently discontinue in patients who are unable to tolerate XALKORI after 2 dose reductions.]
Platelet Count
25 to 50 x 10^9/L with concurrent bleeding | Withhold until recovery to platelet count greater than 50 x 10^9/L and bleeding resolves, then resume at the same dosage.
Less than 25 x 10^9/L | Withhold until recovery to platelet count greater than 50 x 10^9/L, then resume at the next lower dosage. Permanently discontinue for recurrence.
Anemia
Hemoglobin less than 8 g/dL | Withhold until recovery to hemoglobin 8 g/dL or more, then resume at the same dosage.
Life-threatening anemia; urgent intervention indicated. | Withhold until recovery to hemoglobin 8 g/dL or more, then resume at the next lower dosage. Permanently discontinue for recurrence.

Recommended Dosage Modifications for Non-Hematologic Adverse Reactions

The recommended dosage modifications for non-hematologic adverse reactions are provided in Table 8.

Table 8. All Patients: XALKORI Dosage Modification for Non-Hematologic Adverse Reactions
Severity of Adverse Reaction [Grade based on National Cancer Institute (NCI) Common Terminology Criteria for Adverse Events (CTCAE), version 4.0.] | XALKORI Dosage Modification
Hepatotoxicity [see Warnings and Precautions (5.1)]
Alanine aminotransferase (ALT) or aspartate aminotransferase (AST) greater than 5 times upper limit of normal (ULN) with total bilirubin less than or equal to 1.5 times ULN | Withhold until recovery to baseline or less than or equal to 3 times ULN, then resume at next lower dosage.
ALT or AST greater than 3 times ULN with concurrent total bilirubin greater than 1.5 times ULN (in the absence of cholestasis or hemolysis) | Permanently discontinue.
Interstitial Lung Disease (Pneumonitis) [see Warnings and Precautions (5.2)]
Any grade drug-related interstitial lung disease/pneumonitis | Permanently discontinue.
QT Interval Prolongation [see Warnings and Precautions (5.3)]
QT corrected for heart rate (QTc) greater than 500 ms on at least 2 separate electrocardiograms (ECGs) | Withhold until recovery to baseline or to a QTc less than 481 ms, then resume at next lower dosage.
QTc greater than 500 ms or greater than or equal to 60 ms change from baseline with Torsade de pointes or polymorphic ventricular tachycardia or signs/symptoms of serious arrhythmia | Permanently discontinue.
Bradycardia [see Warnings and Precautions (5.4)]
Bradycardia [Adult patients: Heart rate less than 60 beats per minute (bpm); Pediatric patients: Resting heart rate less than the 2.5th percentile per age-specific norms.] (symptomatic, may be severe and medically significant, medical intervention indicated) | Withhold until recovery to a resting heart rate according to the patient’s age (based on the 2.5th percentile per age-specific norms) as follows:; - 1 to less than 2 years: 91 bpm or above - 2 to 3 years: 82 bpm or above - 4 to 5 years: 72 bpm or above - 6 to 8 years: 64 bpm or above - Older than 8 years: 60 bpm or above; Evaluate concomitant medications known to cause bradycardia, as well as antihypertensive medications. If contributing concomitant medication is identified and discontinued, or its dose is adjusted, resume at previous dose upon recovery to asymptomatic bradycardia or to the age-specific heart rate provided above. If no contributing concomitant medication is identified, or if contributing concomitant medications are not discontinued or dose adjusted, resume at reduced dose upon recovery to asymptomatic bradycardia or to the age-specific heart rate provided above.
Bradycardia (life-threatening consequences, urgent intervention indicated) | Permanently discontinue if no contributing concomitant medication is identified. If contributing concomitant medication is identified and discontinued, or its dose is adjusted, resume at the second dose reduction level in Table 4 or 5 upon recovery to asymptomatic bradycardia or to the heart rate criteria listed for management of symptomatic or severe, medically significant bradycardia, with frequent monitoring. Permanently discontinue for recurrence.
Ocular Toxicity, including Visual Loss [see Warnings and Precautions (5.5)]
Visual Symptoms, Grade 1 (mild symptoms) or Grade 2 (moderate symptoms affecting ability to perform age-appropriate activities of daily living) | Monitor symptoms and report any symptoms to an eye specialist. Consider dose reduction for Grade 2 visual disorders.
Visual Loss (Grade 3 or 4 Ocular Disorder, marked decrease in vision) | Discontinue during evaluation of severe visual loss. Permanently discontinue XALKORI for Grade 3 or 4 ocular disorders or severe visual loss if no other cause found on evaluation.
Gastrointestinal Toxicity [Dosage modifications for gastrointestinal toxicity for pediatric patients with ALCL or IMT and young adults with ALCL only.] [see Warnings and Precautions (5.6)]
Nausea (Grade 3: inadequate oral intake for more than 3 days, medical intervention required) | Grade 3 (despite maximum medical therapy): Withhold until resolved, and then resume at the next lower dose level. [Permanently discontinue in patients who are unable to tolerate XALKORI after 2 dose reductions.]
Vomiting (Grade 3: more than 6 episodes in 24 hours for more than 3 days, medical intervention required, i.e., tube feeding or hospitalization; Grade 4: life-threatening consequences, urgent intervention indicated) | Grade 3 or 4 (despite maximum medical therapy): Withhold until resolved, and then resume at the next lower dose level.
Diarrhea (Grade 3: increase of 7 or more stools per day over baseline; incontinence; hospitalization indicated; Grade 4: life-threatening consequences, urgent intervention indicated) | Grade 3 or 4 (despite maximum medical therapy): Withhold until resolved, and then resume at the next lower dose level.

2.7 Dosage Modifications for Moderate and Severe Hepatic Impairment

The recommended dose of XALKORI in patients with moderate hepatic impairment [any aspartate aminotransferase (AST) and total bilirubin greater than 1.5 times the upper limit of normal (ULN) and less than or equal to 3 times ULN] is the first dose reduction shown in Table 4 for adult patients with NSCLC or IMT and Table 5 for pediatric patients with ALCL or IMT and young adults with ALCL [see Use in Specific Populations (8.7), Clinical Pharmacology (12.3)].

The recommended dose of XALKORI in patients with severe hepatic impairment (any AST and total bilirubin greater than 3 times ULN) is the second dose reduction shown in Table 4 for adult patients with NSCLC or IMT and Table 5 for pediatric patients with ALCL or IMT and young adults with ALCL [see Dosage and Administration (2.6), Use in Specific Populations (8.7), Clinical Pharmacology (12.3)].

2.8 Dosage Modification for Severe Renal Impairment

The recommended dosage of XALKORI in patients with severe renal impairment [creatinine clearance (CLcr) less than 30 mL/min, calculated using the modified Cockcroft-Gault equation for adult patients and the Schwartz equation for pediatric patients] not requiring dialysis is the second dose reduction shown in Table 4 for adult patients with NSCLC or IMT and Table 5 for pediatric patients with ALCL or IMT and young adults with ALCL [see Use in Specific Populations (8.7), Clinical Pharmacology (12.3)].

2.9 Dosage Modification for Concomitant Use of Strong CYP3A Inhibitors

Avoid concomitant use of strong CYP3A inhibitors [see Drug Interactions (7.1)]. If concomitant use of strong CYP3A inhibitors is unavoidable, reduce the dose of XALKORI to the second dose reduction shown in Table 4 for adult patients with NSCLC or IMT and Table 5 for pediatric patients with ALCL or IMT and young adults with ALCL. After discontinuation of a strong CYP3A inhibitor, resume the XALKORI dose used prior to initiating the strong CYP3A inhibitor.

3 DOSAGE FORMS AND STRENGTHS

Capsules:

- 200 mg: hard gelatin capsule, size 1, white opaque body and pink opaque cap, with "Pfizer" on the cap and "CRZ 200" on the body.
- 250 mg: hard gelatin capsule, size 0, pink opaque cap and body, with "Pfizer" on the cap and "CRZ 250" on the body.

Oral Pellets:

- 20 mg: hard gelatin capsule, size 4, white opaque body and light blue opaque cap, printed with black ink “Pfizer” on the cap and “CRZ 20” on the body.
- 50 mg: hard gelatin capsule, size 3, light gray opaque body and gray opaque cap, printed with black ink “Pfizer” on the cap and “CRZ 50” on the body.
- 150 mg: hard gelatin capsule, size 0, light blue opaque body and cap, printed with black ink “Pfizer” on the cap and “CRZ 150” on the body.

4 CONTRAINDICATIONS

None.

5 WARNINGS AND PRECAUTIONS

5.1 Hepatotoxicity

Drug-induced hepatotoxicity with fatal outcome occurred in 0.1% of the 1719 patients treated with XALKORI for NSCLC across clinical trials [see Adverse Reactions (6.1)]. Concurrent elevations in ALT or AST ≥3 times the ULN and total bilirubin ≥2 times the ULN, with normal alkaline phosphatase, occurred in <1% of patients treated with XALKORI. Increased ALT or AST >5 times the ULN occurred in 11% and 6% of patients, respectively. One percent (1.0%) of patients required permanent discontinuation due to elevated transaminases. Increased transaminases generally occurred within the first 2 months of treatment.

In Study ADVL0912, of 121 patients ages 1 to ≤21 years treated with XALKORI for relapsed or refractory tumors including ALCL and IMT, 71% and 79% had increases of AST and ALT, respectively, with increased ALT or AST >5 times the ULN in 6% each. Of the 26 patients with ALCL treated with XALKORI, 65% and 81% had increases of AST and ALT, respectively, with increases >5 times the ULN in 4% each. Of the 14 pediatric patients with IMT treated with XALKORI, 71% had increases of AST and 71% had increases of ALT.

In Study A8081013, of the 7 adult patients with IMT treated with XALKORI, 57% and 43% had increases of AST and ALT, respectively.

Monitor liver function tests, including ALT, AST, and total bilirubin, every 2 weeks during the first 2 months of treatment, then once a month, and as clinically indicated, with more frequent repeat testing for increased liver transaminases, alkaline phosphatase, or total bilirubin in patients who develop increased transaminases. Withhold, reduce dose, or permanently discontinue XALKORI for hepatotoxicity as recommended [see Dosage and Administration (2.6)].

5.2 Interstitial Lung Disease/Pneumonitis

Severe, life-threatening, or fatal interstitial lung disease (ILD)/pneumonitis can occur in patients treated with XALKORI. Across clinical trials in patients with NSCLC (n=1719), 2.9% of XALKORI-treated patients had ILD of any grade, 1% had Grade 3 or 4 ILD, and 0.5% had fatal ILD [see Adverse Reactions (6.1)]. Interstitial lung disease generally occurred within 3 months after the initiation of XALKORI.

In Study ADVL0912, among 121 patients ages 1 to ≤21 years with relapsed or refractory tumors, including ALCL and IMT, ILD occurred in 0.8% of patients.

Monitor patients for pulmonary symptoms indicative of ILD/pneumonitis. Exclude other potential causes of ILD/pneumonitis, and permanently discontinue XALKORI in patients diagnosed with drug-related ILD/pneumonitis [see Dosage and Administration (2.6)].

5.3 QT Interval Prolongation

QTc prolongation can occur in patients treated with XALKORI. Across clinical trials in patients with NSCLC, 2.1% of 1616 patients had QTcF (corrected QT for heart rate by the Fridericia method) greater than or equal to 500 ms and 5% of 1582 patients had an increase from baseline QTcF greater than or equal to 60 ms by automated machine-read evaluation of ECGs.

In Study ADVL0912, QTc prolongation was reported as an adverse reaction in 4.1% of patients, including 8% of patients with ALCL and 7% of pediatric patients with IMT.

Avoid use of XALKORI in patients with congenital long QT syndrome. Monitor ECGs and electrolytes in patients with congestive heart failure, bradyarrhythmias, electrolyte abnormalities, or who are taking medications that are known to prolong the QT interval. Withhold, reduce dose, or permanently discontinue XALKORI for QT/QTc interval prolongation as recommended [see Dosage and Administration (2.6), Clinical Pharmacology (12.2)].

5.4 Bradycardia

Symptomatic bradycardia can occur in patients receiving XALKORI. Across clinical trials in patients with NSCLC, bradycardia occurred in 13% of 1719 patients treated with XALKORI. Grade 3 syncope occurred in 2.4% of XALKORI-treated patients and in 0.6% of the chemotherapy-treated patients [see Adverse Reactions (6.1)].

In Study ADVL0912, among 121 patients ages 1 to ≤21 years treated with XALKORI, bradycardia was reported in 14%, including Grade 3 bradycardia in 0.8% of patients. Of the 26 patients with ALCL treated with XALKORI, bradycardia (all Grade 1) was reported in 19%. Of the 14 pediatric patients with IMT treated with XALKORI, bradycardia was reported in 14% of patients, including Grade 3 bradycardia in 7% of patients.

Avoid using XALKORI in combination with other medications known to cause bradycardia (e.g., beta-blockers, nondihydropyridine-calcium channel blockers, clonidine, and digoxin) to the extent possible. Monitor heart rate and blood pressure regularly. If bradycardia occurs, re-evaluate for the use of concomitant medications known to cause bradycardia. Withhold, reduce dose, or permanently discontinue XALKORI for bradycardia as recommended [see Dosage and Administration (2.6)].

5.5 Severe Visual Loss

Across all clinical trials in patients with NSCLC, the incidence of Grade 4 visual field defect with visual loss was 0.2% of 1719 patients [see Adverse Reactions (6.1)]. Optic atrophy and optic nerve disorder have been reported as potential causes of visual loss.

In Study ADVL0912, visual disorders occurred in 46% of 121 patients with XALKORI, including 65% of 26 patients with ALCL and 50% of 14 patients with IMT. Of the 56 patients who experienced visual disorders, one pediatric patient with IMT experienced Grade 3 myopic optic nerve disorder. The most common visual symptoms were blurred vision and visual impairment.

Assessment of visual symptoms for all patients is recommended monthly during treatment. Report new visual symptoms to an eye specialist.

For pediatric and young adult patients with ALCL or pediatric patients with IMT, obtain baseline and follow-up ophthalmologic examinations including retinal examination within 1 month of starting XALKORI and every 3 months thereafter. The ophthalmological evaluation should consist of best corrected visual acuity, retinal photographs, visual fields, optical coherence tomography (OCT), and other evaluations as appropriate [see Dosage and Administration (2.6), Adverse Reactions (6.1)].

Permanently discontinue XALKORI for Grade 3 or 4 ocular disorders or severe visual loss (best corrected vision less than 20/200 in one or both eyes) unless another cause is identified [see Dosage and Administration (2.6)]. There is insufficient information to characterize the risks of resumption of XALKORI in patients who develop visual symptoms or visual loss. A decision to resume XALKORI should consider the potential benefits versus risks to the patient.

5.6 Gastrointestinal Toxicity in Pediatric and Young Adult Patients with ALCL or Pediatric Patients with IMT

XALKORI can cause severe gastrointestinal toxicities in pediatric and young adult patients with ALCL or pediatric patients with IMT [see Adverse Reactions (6.1)]. In patients with ALCL (n=26), gastrointestinal toxicity occurred in 100% of patients; Grade 3 gastrointestinal toxicity occurred in 27% of patients and included diarrhea, nausea, vomiting, and stomatitis. In pediatric patients with IMT (n=14), vomiting occurred in 93%, nausea occurred in 86%, and diarrhea occurred in 64% of patients.

Provide standard antiemetic and antidiarrheal agents for gastrointestinal toxicities in pediatric and young adult patients with ALCL or pediatric patients with IMT. Antiemetics are recommended prior to and during treatment with XALKORI to prevent nausea and vomiting. If patients develop Grade 3 nausea lasting 3 days or Grade 3 or 4 diarrhea or vomiting despite maximum medical therapy, withhold XALKORI until resolved, and then resume at the next lower dose level. Consider supportive care such as hydration, electrolyte supplementation, and nutritional support as clinically indicated [see Dosage and Administration (2.6)].

5.7 Embryo-Fetal Toxicity

Based on its mechanism of action, XALKORI can cause fetal harm when administered to a pregnant woman. In animal reproduction studies, oral administration of crizotinib in pregnant rats during organogenesis at exposures similar to those observed with the maximum recommended human dose resulted in embryotoxicity and fetotoxicity. Advise pregnant women and females of reproductive potential of the potential risk to a fetus. Advise females of reproductive potential to use effective contraception during treatment with XALKORI and for 45 days following the last dose. Advise male patients with female partners of reproductive potential to use condoms during treatment with XALKORI and for 90 days after the last dose [see Use in Specific Populations (8.1, 8.3), Nonclinical Toxicology (13.1)].

6 ADVERSE REACTIONS

The following clinically significant adverse reactions are described elsewhere in the labeling:

- Hepatotoxicity [see Warnings and Precautions (5.1)]
- Interstitial Lung Disease/Pneumonitis [see Warnings and Precautions (5.2)]
- QT Interval Prolongation [see Warnings and Precautions (5.3)]
- Bradycardia [see Warnings and Precautions (5.4)]
- Severe Visual Loss [see Warnings and Precautions (5.5)]
- Gastrointestinal Toxicity in Pediatric and Young Adult Patients with ALCL or Pediatric Patients with IMT [see Warnings and Precautions (5.6)]

6.1 Clinical Trials Experience

Because clinical trials are conducted under widely varying conditions, adverse reaction rates observed in the clinical trials of a drug cannot be directly compared to rates in the clinical trials of another drug and may not reflect the rates observed in clinical practice.

The data in the Warnings and Precautions reflect exposure to XALKORI in 1719 patients with NSCLC who received XALKORI 250 mg twice daily enrolled on Studies 1 (including an additional 109 patients who crossed over from the control arm), 2, 3, a single-arm trial (n=1063) of ALK-positive NSCLC, and an additional ALK-positive NSCLC expansion cohort of a dose finding study (n=154). The data also reflect exposure to XALKORI in 121 patients ages 1 to ≤21 years with relapsed or refractory tumors, including 26 patients with systemic ALCL and 14 pediatric patients with IMT, in a single-arm trial (Study ADVL0912). The data are also described for 7 adult patients with IMT treated with XALKORI in a single-arm trial (Study A8081013).

ALK- or ROS1-Positive Metastatic NSCLC

The data described below is based primarily on 343 patients with ALK-positive metastatic NSCLC who received XALKORI 250 mg orally twice daily from 2 open-label, randomized, active-controlled trials (Studies 1 and 2). The safety of XALKORI was also evaluated in 50 patients with ROS1-positive metastatic NSCLC from a single-arm study (Study 3).

The most common adverse reactions (≥25%) of XALKORI in patients with NSCLC are vision disorders, nausea, diarrhea, vomiting, edema, constipation, elevated transaminases, fatigue, decreased appetite, upper respiratory infection, dizziness, and neuropathy.

Previously Untreated ALK-Positive Metastatic NSCLC - Study 1 (PROFILE 1014)

The data in Table 9 are derived from 340 patients with ALK-positive metastatic NSCLC who had not received previous systemic treatment for advanced disease who received treatment in a randomized, multicenter, open-label, active-controlled trial (Study 1). Patients in the XALKORI arm (n=171) received XALKORI 250 mg orally twice daily until documented disease progression, intolerance to therapy, or the investigator determined that the patient was no longer experiencing clinical benefit. A total of 169 patients in the chemotherapy arm received pemetrexed 500 mg/m^2 with cisplatin 75 mg/m^2 (n=91) or carboplatin at a dose calculated to produce an AUC of 5 or 6 mg×min/mL (n=78). Chemotherapy was given by intravenous infusion every 3 weeks for up to 6 cycles, in the absence of dose-limiting chemotherapy-related toxicities. After 6 cycles, patients remained on study with no additional anticancer treatment, and tumor assessments continued until documented disease progression.

The median duration of study treatment was 10.9 months for patients in the XALKORI arm and 4.1 months for patients in the chemotherapy arm. Median duration of treatment was 5.2 months for patients who received XALKORI after cross over from chemotherapy. Across the 340 patients who were treated in Study 1, the median age was 53 years; 16% of patients were older than 65 years. A total of 62% of patients were female and 46% were Asian.

Serious adverse events were reported in 34% of patients treated with XALKORI. The most frequent serious adverse events reported in patients treated with XALKORI were dyspnea (4.1%) and pulmonary embolism (2.9%). Fatal adverse events in XALKORI-treated patients occurred in 2.3% patients, consisting of septic shock, acute respiratory failure, and diabetic ketoacidosis.

Dose reductions due to adverse reactions were required in 6% of XALKORI-treated patients. The most frequent adverse reactions that led to dose reduction in these patients were nausea (1.8%) and elevated transaminases (1.8%).

Permanent discontinuation of XALKORI treatment for adverse reactions was 8%. The most frequent adverse reactions that led to permanent discontinuation in XALKORI-treated patients were elevated transaminases (1.2%), hepatotoxicity (1.2%), and ILD (1.2%).

Tables 9 and 10 summarize common adverse reactions and laboratory abnormalities in XALKORI-treated patients.

Table 9. Adverse Reactions Reported at a Higher Incidence (≥5% Higher for All Grades or ≥2% Higher for Grades 3–4) with XALKORI than Chemotherapy in Study 1 [Adverse reactions were graded using NCI CTCAE version 4.0. Includes cases reported within the clustered terms:]
Adverse Reaction | XALKORI (N=171) |  | Chemotherapy (Pemetrexed/Cisplatin or Pemetrexed/Carboplatin) (N=169)
Adverse Reaction | All Grades (%) | Grade 3–4 (%) | All Grades (%) | Grade 3–4 (%)
Cardiac
Bradycardia [Bradycardia (Bradycardia, Sinus bradycardia).] | 14 | 1 | 1 | 0
Electrocardiogram QT prolonged | 6 | 2 | 2 | 0
Eye
Vision disorder [Vision Disorder (Diplopia, Photophobia, Photopsia, Reduced visual acuity, Blurred vision, Vitreous floaters, Visual impairment).] | 71 | 1 | 10 | 0
Gastrointestinal
Diarrhea | 61 | 2 | 13 | 1
Vomiting | 46 | 2 | 36 | 3
Constipation | 43 | 2 | 30 | 0
Abdominal pain [Abdominal pain (Abdominal discomfort, Abdominal pain, Lower abdominal pain, Upper abdominal pain, Abdominal tenderness).] | 26 | 0 | 12 | 0
Dyspepsia | 14 | 0 | 2 | 0
Dysphagia | 10 | 1 | 2 | 1
Esophagitis [Esophagitis (Esophagitis, Esophageal ulcer).] | 6 | 2 | 1 | 0
General
Edema [Edema (Edema, Peripheral edema, Face edema, Generalized edema, Local swelling, Periorbital edema).] | 49 | 1 | 12 | 1
Pyrexia | 19 | 0 | 11 | 1
Infections
Upper respiratory infection [Upper respiratory infection (Nasopharyngitis, Pharyngitis, Rhinitis, Upper respiratory tract infection).] | 32 | 0 | 12 | 1
Investigations
Increased weight | 8 | 1 | 2 | 0
Musculoskeletal and Connective Tissue
Pain in extremity | 16 | 0 | 7 | 0
Muscle spasm | 8 | 0 | 2 | 1
Nervous System
Dysgeusia | 26 | 0 | 5 | 0
Headache | 22 | 1 | 15 | 0
Dizziness [Dizziness (Balance disorder, Dizziness, Postural dizziness, Presyncope).] | 18 | 0 | 10 | 1

Additional adverse reactions occurring at an overall incidence between 1% and 60% in patients treated with XALKORI included nausea (56%), decreased appetite (30%), fatigue (29%), neuropathy (21%; gait disturbance, hypoesthesia, muscular weakness, neuralgia, neuropathy peripheral, paresthesia, peripheral sensory neuropathy, polyneuropathy, sensory disturbance), rash (11%), renal cyst (5%), ILD (1%; ILD, pneumonitis), syncope (1%), and decreased blood testosterone (1%; hypogonadism).

Clinically relevant adverse reactions in <1% of patients who received XALKORI included photosensitivity (0.3%).

Table 10. Laboratory Abnormalities with Grades 3–4 Occurring in ≥4% of XALKORI-Treated Patients in Study 1
 | XALKORI |  | Chemotherapy
Laboratory Abnormality | Any Grade (%) | Grade 3–4 (%) | Any Grade (%) | Grade 3–4 (%)
Hematology
Neutropenia | 52 | 11 | 59 | 16
Lymphopenia | 48 | 7 | 53 | 13
Chemistry
Increased ALT | 79 | 15 | 33 | 2
Increased AST | 66 | 8 | 28 | 1
Hypophosphatemia | 32 | 10 | 21 | 6
Additional laboratory test abnormality in patients treated with XALKORI was an increase in creatinine (Any Grade: 99%; Grade 3: 2%; Grade 4: 0%) compared to the chemotherapy arm (Any Grade: 92%; Grade 3: 0%; Grade 4: 1%).

Previously Treated ALK-Positive Metastatic NSCLC - Study 2 (PROFILE 1007)

The data in Table 11 are derived from 343 patients with ALK-positive metastatic NSCLC enrolled in a randomized, multicenter, active-controlled, open-label trial (Study 2). Patients in the XALKORI arm (n=172) received XALKORI 250 mg orally twice daily until documented disease progression, intolerance to therapy, or the investigator determined that the patient was no longer experiencing clinical benefit. A total of 171 patients in the chemotherapy arm received pemetrexed 500 mg/m^2 (n=99) or docetaxel 75 mg/m^2 (n=72) by intravenous infusion every 3 weeks until documented disease progression, intolerance to therapy, or the investigator determined that the patient was no longer experiencing clinical benefit. Patients in the chemotherapy arm received pemetrexed unless they had received pemetrexed as part of first-line or maintenance treatment.

The median duration of study treatment was 7.1 months for patients who received XALKORI and 2.8 months for patients who received chemotherapy. Across the 347 patients who were randomized to study treatment (343 received at least 1 dose of study treatment), the median age was 50 years; 14% of patients were older than 65 years. A total of 56% of patients were female and 45% of patients were Asian.

Serious adverse reactions were reported in 37% of patients treated with XALKORI and 23% of patients in the chemotherapy arm. The most frequent serious adverse reactions reported in patients treated with XALKORI were pneumonia (4.1%), pulmonary embolism (3.5%), dyspnea (2.3%), and ILD (2.9%). Fatal adverse reactions in XALKORI-treated patients in Study 2 occurred in 5% of patients, consisting of: acute respiratory distress syndrome, arrhythmia, dyspnea, pneumonia, pneumonitis, pulmonary embolism, ILD, respiratory failure, and sepsis.

Dose reductions due to adverse reactions were required in 16% of XALKORI-treated patients. The most frequent adverse reactions that led to dose reduction in the patients treated with XALKORI were increased ALT (8%) including some patients with concurrent increased AST, QTc prolongation (2.9%), and neutropenia (2.3%).

XALKORI was discontinued for adverse reactions in 15% of patients. The most frequent adverse reactions that led to discontinuation of XALKORI were ILD (1.7%), increased ALT and AST (1.2%), dyspnea (1.2%), and pulmonary embolism (1.2%).

Tables 11 and 12 summarize common adverse reactions and laboratory abnormalities, respectively, in XALKORI-treated patients.

Table 11. Adverse Reactions Reported at a Higher Incidence (≥5% Higher for All Grades or ≥2% Higher for Grades 3–4) with XALKORI than Chemotherapy in Study 2 [Adverse reactions were graded using NCI CTCAE version 4.0. Includes cases reported within the clustered terms:]
Adverse Reaction | XALKORI (N=172) |  | Chemotherapy (Pemetrexed or Docetaxel) (N=171)
Adverse Reaction | All Grades (%) | Grade 3–4 (%) | All Grades (%) | Grade 3–4 (%)
Nervous System
Dysgeusia | 26 | 0 | 9 | 0
Dizziness [Dizziness (Balance disorder, Dizziness, Postural dizziness).] | 22 | 1 | 8 | 0
Syncope | 3 | 3 | 0 | 0
Eye
Vision disorder [Vision Disorder (Diplopia, Photophobia, Photopsia, Blurred vision, Reduced visual acuity, Visual impairment, Vitreous floaters).] | 60 | 0 | 9 | 0
Cardiac
Electrocardiogram QT prolonged | 5 | 3 | 0 | 0
Bradycardia [Bradycardia (Bradycardia, Sinus bradycardia).] | 5 | 0 | 0 | 0
Investigations
Decreased weight | 10 | 1 | 4 | 0
Gastrointestinal
Diarrhea | 60 | 0 | 19 | 1
Nausea | 55 | 1 | 37 | 1
Vomiting | 47 | 1 | 18 | 0
Constipation | 42 | 2 | 23 | 0
Dyspepsia | 8 | 0 | 3 | 0
Infections
Upper respiratory infection [Upper respiratory infection (Laryngitis, Nasopharyngitis, Pharyngitis, Rhinitis, Upper respiratory tract infection).] | 26 | 0 | 13 | 1
Respiratory, Thoracic and Mediastinal
Pulmonary embolism [Pulmonary embolism (Pulmonary artery thrombosis, Pulmonary embolism).] | 6 | 5 | 2 | 2
General
Edema [Edema (Face edema, Generalized edema, Local swelling, Localized edema, Edema, Peripheral edema, Periorbital edema).] | 31 | 0 | 16 | 0

Additional adverse reactions occurring at an overall incidence between 1% and 30% in patients treated with XALKORI included decreased appetite (27%), fatigue (27%), neuropathy (19%; dysesthesia, gait disturbance, hypoesthesia, muscular weakness, neuralgia, peripheral neuropathy, paresthesia, peripheral sensory neuropathy, polyneuropathy, burning sensation in skin), rash (9%), ILD (4%; acute respiratory distress syndrome, ILD, pneumonitis), renal cyst (4%), esophagitis (2%), hepatic failure (1%), and decreased blood testosterone (1%; hypogonadism).

Clinically relevant adverse reactions in <1% of patients who received XALKORI included photosensitivity (0.4%).

Table 12. Laboratory Abnormalities with Grades 3–4 Occurring in ≥4% of XALKORI-Treated Patients in Study 2
 | XALKORI |  | Chemotherapy
Laboratory Abnormality | Any Grade (%) | Grade 3–4 (%) | Any Grade (%) | Grade 3–4 (%)
Hematology
Lymphopenia | 51 | 9 | 60 | 25
Neutropenia | 49 | 12 | 28 | 12
Chemistry
Increased ALT | 76 | 17 | 38 | 4
Increased AST | 61 | 9 | 33 | 0
Hypophosphatemia | 28 | 5 | 25 | 6
Hypokalemia | 18 | 4 | 10 | 1
Additional laboratory test abnormality in patients treated with XALKORI was an increase in creatinine (Any Grade: 96%; Grade 3: 1%; Grade 4: 0%) compared to the chemotherapy arm (Any Grade: 72%; Grade 3: 0%; Grade 4: 0%).

ROS1-Positive Metastatic NSCLC - Study 3 (PROFILE 1001)

The safety profile of XALKORI from Study 3, which was evaluated in 50 patients with ROS1-positive metastatic NSCLC, was generally consistent with the safety profile of XALKORI evaluated in patients with ALK-positive metastatic NSCLC (n=1669). Vision disorders occurred in 92% of patients in Study 3; 90% were Grade 1 and 2% were Grade 2. The median duration of exposure to XALKORI was 34.4 months.

Description of Selected Adverse Reactions in Patients with Metastatic NSCLC

Vision disorders: Vision disorders, most commonly visual impairment, photopsia, blurred vision, or vitreous floaters, occurred in 63% of 1719 patients. The majority (95%) of these patients had Grade 1 visual adverse reactions. There were 0.8% of patients with Grade 3 and 0.2% of patients with Grade 4 visual impairment. Based on the Visual Symptom Assessment Questionnaire (VSAQ-ALK), patients treated with XALKORI in Studies 1 and 2 reported a higher incidence of visual disturbances compared to patients treated with chemotherapy. The onset of vision disorder generally was within the first week of drug administration. The majority of patients on the XALKORI arms in Studies 1 and 2 (>50%) reported visual disturbances which occurred at a frequency of 4–7 days each week, lasted up to 1 minute, and had mild or no impact (scores 0 to 3 out of a maximum score of 10) on daily activities as captured in the VSAQ-ALK questionnaire.

Neuropathy: Neuropathy, most commonly sensory in nature, occurred in 25% of 1719 patients. Most events (95%) were Grade 1 or Grade 2 in severity.

Renal cysts: Renal cysts were experienced by 3.0% of 1719 patients. The majority of renal cysts in XALKORI-treated patients were complex. Local cystic invasion beyond the kidney occurred, in some cases with imaging characteristics suggestive of abscess formation. However, across clinical trials no renal abscesses were confirmed by microbiology tests.

Renal toxicity: The estimated glomerular filtration rate (eGFR) decreased from a baseline median of 96.42 mL/min/1.73 m^2 (n=1681) to a median of 80.23 mL/min/1.73 m^2 at 2 weeks (n=1499) in patients with ALK-positive advanced NSCLC who received XALKORI in clinical trials. No clinically relevant changes occurred in median eGFR from 12 to 104 weeks of treatment. Median eGFR slightly increased (83.02 mL/min/1.73 m^2) 4 weeks after the last dose of XALKORI. Overall, 76% of patients had a decrease in eGFR to <90 mL/min/1.73 m^2, 38% had a decrease to eGFR to <60 mL/min/1.73 m^2, and 3.6% had a decrease to eGFR to <30 mL/min/1.73 m^2.

Relapsed or Refractory, Systemic ALK-Positive ALCL - Study ADVL0912

The safety of XALKORI was evaluated in Study ADVL0912 [see Clinical Studies 14.2], which included 26 patients with relapsed or refractory, systemic ALCL after at least one systemic therapy. Eligible patients were 1 to ≤21 years of age and were required to have an absolute neutrophil count ≥1000/mm^3 (750/mm^3 if bone marrow was involved), platelet count ≥75,000/mm^3 (25,000/mm^3 if bone marrow was involved), creatinine clearance ≥70ml/min/1.73m^2, and QTc ≤480 msec. The study excluded patients with ALT >2.5 times upper limit of normal (ULN), bilirubin ≤1.5 times ULN, and central nervous system tumors.

Patients with ALCL received XALKORI 165 mg/m^2 or 280 mg/m^2 orally twice daily until disease progression or unacceptable toxicity. The median duration of exposure was 5.4 months (range 1.8, 82.3 months), with 46% of patients treated for at least 6 months and 35% of patients treated for at least 12 months.

Serious adverse reactions occurred in 35% of patients with ALCL treated with XALKORI. The most frequent serious adverse reactions were neutropenia (12%) and hypotension (8%).

Dose interruptions and dose reductions occurred in 77% and 19% of patients with ALCL, respectively. XALKORI was discontinued for an adverse reaction in 8% of patients.

The most common adverse reactions (≥35%), excluding laboratory abnormalities, were diarrhea, vomiting, nausea, vision disorder, headache, musculoskeletal pain, stomatitis, fatigue, decreased appetite, pyrexia, abdominal pain, cough, and pruritis.

The most common Grade 3 or 4 laboratory abnormalities (≥15%) included neutropenia, lymphopenia, and thrombocytopenia. Grade 4 laboratory abnormalities (≥15%) included neutropenia (62%), lymphopenia (35%), and thrombocytopenia (19%).

Selected adverse reactions are summarized in Table 13.

Table 13. Adverse Reactions in ≥20% of Patients with Systemic ALCL in Study ADVL0912
Adverse Reaction | XALKORI N=26
Adverse Reaction | All Grades (%) | Grade 3–4 (%)
Blood and Lymphatic System Disorders [Derived from laboratory values collected in Cycle 1 and adverse reaction data.]
Neutropenia [Includes neutrophil count decreased.] | 100 | 77
Lymphopenia [Includes lymphocyte count decreased.] | 58 | 38
Anemia | 54 | 3.8
Thrombocytopenia [Includes platelet count decreased.] | 38 | 19
Gastrointestinal Disorders
Diarrhea | 92 | 12
Vomiting | 92 | 3.8
Nausea | 77 | 3.8
Abdominal Pain | 50 | 0
Stomatitis [Includes oral pain, oropharyngeal pain, stomatitis.] | 46 | 8
Constipation | 31 | 0
Renal Disorders
Blood creatinine increased | 100 | 0
Investigations
ALT increased | 81 | 3.8
AST increased | 65 | 3.8
Hypocalcemia | 62 | 3.8
Hypoalbuminemia | 54 | 0
Hyperglycemia | 46 | 0
Hypomagnesemia | 46 | 0
Hypoglycemia | 35 | 0
Hypokalemia | 31 | 3.8
Hypermagnesemia | 27 | 0
Hyperkalemia | 23 | 0
Nervous System Disorders
Headache | 58 | 3.8
Dysgeusia | 23 | 0
Dizziness | 23 | 0
Eye Disorders
Vision disorders [Includes blurred vision, visual impairment, photophobia, photopsia, reduced visual acuity, vitreous floaters, cyanopsia, heterophoria, visual field defect.] | 65 | 0
Musculoskeletal Disorders
Musculoskeletal pain [Includes arthralgia, back pain, myalgia, non-cardiac chest pain, pain in extremity.] | 58 | 12
General Disorders
Fatigue | 46 | 0
Pyrexia | 38 | 0
Edema [Includes peripheral edema, face edema, periorbital edema, localized edema.] | 27 | 0
Chills | 23 | 0
Metabolism and Nutrition Disorders
Decreased appetite | 42 | 0
Skin and Subcutaneous Disorders
Pruritus | 35 | 0
Rash [Includes rash maculopapular, rash pustular.] | 23 | 0
Infections
Upper respiratory tract infection [Includes upper respiratory tract infection, pharyngitis, rhinitis, sinusitis.] | 31 | 0
Respiratory Disorders
Cough | 35 | 0
Rhinitis allergic | 23 | 0
Vascular Disorders
Hypertension | 31 | 0
Adverse reactions were graded using NCI CTCAE version 4.0.

Clinically relevant adverse reactions in <20% of patients treated with XALKORI included:

- Cardiac disorders: Bradycardia (19%), electrocardiogram QT prolonged (8%)
- Vascular disorders: Hypotension (19%)
- Investigations: Alkaline phosphatase increase (19%), hypernatremia (19%), GGT increase (8%), hyponatremia (12%), hyperuricemia (12%), hypophosphatemia (12%)
- Nervous system disorders: Peripheral neuropathy (12%)
- Gastrointestinal disorders: Esophagitis (8%)
- Blood and lymphatic disorders: Febrile neutropenia (3.8%)
- Musculoskeletal disorders: Muscular weakness (8%)
- Renal disorders: Acute renal injury (8%)

Unresectable, Recurrent, or Refractory ALK-Positive IMT

Study ADVL0912

The safety of XALKORI was evaluated in Study ADVL0912 [see Clinical Studies (14.3)] that included 14 pediatric patients with unresectable, recurrent, or refractory IMT.

Pediatric patients with IMT received XALKORI 280 mg/m^2 orally twice daily until disease progression or unacceptable toxicity. Two patients received a lower dose. The median duration of treatment with XALKORI was 20.5 months.

Serious adverse reactions occurred in 7% of pediatric patients with IMT treated with XALKORI. The most frequent serious adverse reaction was neutropenia and hypotension (7% for each).

Dose interruptions due to an adverse reaction occurred in 71% of patients. Dose reductions due to an adverse reaction occurred in 29% of patients. Permanent discontinuation occurred in 29% of patients.

The most common adverse reactions (≥35%) were vomiting, nausea, diarrhea, abdominal pain, rash, vision disorder, upper respiratory tract infection, cough, pyrexia, musculoskeletal pain, fatigue, edema, constipation, and headache.

The most common Grade 3 or 4 laboratory abnormality (>15%) was neutropenia.

Table 14 and Table 15 summarize the adverse reactions and laboratory abnormalities, respectively, in Study ADVL0912.

Table 14. Adverse Reactions in ≥20% of Pediatric Patients with IMT Treated With XALKORI in Study ADVL0912
Adverse Reaction | XALKORI N=14
 | All Grades (%) | Grade 3–4 (%)
Gastrointestinal Disorders
Vomiting | 93 | 0
Nausea | 86 | 0
Diarrhea | 64 | 7
Abdominal pain [Includes abdominal pain and abdominal pain upper.] | 57 | 0
Constipation | 36 | 0
Stomatitis [Includes oral pain and oropharyngeal pain.] | 29 | 0
Infections
Upper respiratory tract infection [Includes upper respiratory tract infection, pharyngitis, rhinitis.] | 64 | 0
Skin Infection | 29 | 0
Respiratory Disorders
Cough [Includes cough and productive cough.] | 64 | 0
Rhinitis allergic | 29 | 0
Skin and Subcutaneous Disorders
Rash [Includes rash maculopapular, rash pustular, dermatitis acneiform.] | 57 | 0
General Disorders
Pyrexia | 50 | 0
Fatigue | 43 | 0
Edema [Includes face edema, localized edema, periorbital edema, peripheral edema.] | 36 | 7
Pain [Includes pain, bone pain, ear pain.] | 29 | 0
Eye Disorders
Vision disorders [Includes photophobia, photopsia, vision blurred, visual impairment, vitreous floaters.] | 50 | 0
Musculoskeletal Disorders
Musculoskeletal pain [Includes arthralgia, myalgia, non-cardiac chest pain, pain in extremity.] | 43 | 0
Nervous System Disorders
Headache | 36 | 0
Metabolism and Nutrition Disorders
Decreased appetite | 29 | 0
Vascular Disorders
Hypotension | 21 | 7
Adverse reactions were graded using NCI CTCAE version 4.0.

Clinically relevant adverse reactions in <20% of pediatric patients with IMT treated with XALKORI included:

Cardiac disorders: Bradycardia (14%), electrocardiogram QT prolonged (7%)

Gastrointestinal disorders: Dyspepsia (14%), esophagitis (7%)

Vascular disorders: Hypertension (14%)

Nervous system disorders: Peripheral neuropathy (7%)

Blood and lymphatic disorders: Febrile neutropenia (7%)

Musculoskeletal disorders: Muscular weakness (7%)

Table 15. Laboratory Abnormalities (≥15%) That Worsened from Baseline in Pediatric Patients with IMT Treated With XALKORI in Study ADVL0912
Laboratory Abnormality | XALKORI [The incidence is based on the number of patients who had both a baseline and at least one on-study laboratory measurement and varied from 13 to 14.] , [Laboratory abnormality data were only collected for the 1st cycle (28 days) of treatment for the duration of the study.]
Laboratory Abnormality | Any Grade (%) | Grade 3–4 (%)
Chemistry
Increased creatinine | 100 | 0
Decreased calcium | 36 | 0
Increased magnesium | 23 | 0
Decreased phosphate | 15 | 0
Hematology
Decreased neutrophils | 64 | 36
Hepatic
Increased ALT | 36 | 0

Study A8081013

The safety of XALKORI for adult patients with ALK-positive IMT was evaluated in Study A8081013 [see Clinical Studies (14.3)] that included 7 patients with IMT with a median age of 38 years (range 23 to 73). The safety profile of this patient group was generally consistent with the safety profile of XALKORI evaluated in patients with ALK-positive or ROS1-positive NSCLC.

The most frequent adverse reactions (≥20%) were vision disorders, nausea, and edema.

6.2 Postmarketing Experience

The following additional adverse reaction has been identified during post-approval use of XALKORI. Because this reaction is reported voluntarily from a population of uncertain size, it is not always possible to reliably estimate the frequency or establish a causal relationship to drug exposure.

Investigations: Increased blood creatine phosphokinase

7 DRUG INTERACTIONS

7.1 Effect of Other Drugs on XALKORI

Strong or Moderate CYP3A Inhibitors

Concomitant use of crizotinib with strong CYP3A inhibitors increases crizotinib plasma concentrations [see Clinical Pharmacology (12.3)], which may increase the risk of adverse reactions of XALKORI. Avoid concomitant use of strong CYP3A inhibitors. If concomitant use of strong CYP3A inhibitors is unavoidable, reduce the XALKORI dosage [see Dosage and Administration (2.9)]. Avoid grapefruit or grapefruit juice which may also increase plasma concentrations of crizotinib. Use caution with concomitant use of moderate CYP3A inhibitors.

Strong CYP3A Inducers

Concomitant use of crizotinib with strong CYP3A inducers decreases crizotinib plasma concentrations [see Clinical Pharmacology (12.3)], which may decrease the efficacy of XALKORI. Avoid concomitant use of strong CYP3A inducers.

7.2 Effect of XALKORI on Other Drugs

CYP3A Substrates

Concomitant use of crizotinib increases plasma concentrations of CYP3A substrates [see Clinical Pharmacology (12.3)], which may increase the risk of adverse reactions of these substrates. Avoid concomitant use of XALKORI with CYP3A substrates where minimal concentration changes may lead to serious adverse reactions. If concomitant use of XALKORI is unavoidable, decrease the CYP3A substrate dosage in accordance with approved product labeling.

7.3 Drugs That Prolong the QT Interval

XALKORI can prolong the QT/QTc interval. Avoid concomitant use of XALKORI with drugs that prolong the QT interval [see Warnings and Precautions (5.3), Clinical Pharmacology (12.2)].

7.4 Drugs That Cause Bradycardia

XALKORI can cause bradycardia. Avoid concomitant use of XALKORI with drugs that cause bradycardia (e.g., beta-blockers, non-dihydropyridine calcium channel blockers, clonidine, and digoxin) [see Warnings and Precautions (5.4)].

8 USE IN SPECIFIC POPULATIONS

8.1 Pregnancy

Risk Summary

Based on findings from animal studies and its mechanism of action, XALKORI can cause fetal harm when administered to a pregnant woman [see Clinical Pharmacology (12.1)]. There are no available data on the use of XALKORI in pregnant women. In animal reproduction studies, oral administration of crizotinib to pregnant rats during organogenesis at exposures similar to those expected with the maximum recommended human dose resulted in embryotoxicity and fetotoxicity (see Data). Advise pregnant women of the potential risk to a fetus.

In the U.S. general population, the estimated background risk of major birth defects and miscarriage in clinically recognized pregnancies is 2% to 4% and 15% to 20%, respectively.

Data

Animal Data

Crizotinib was administered to pregnant rats and rabbits during organogenesis to study the effects on embryo-fetal development. Postimplantation loss was increased at doses ≥50 mg/kg/day (approximately 0.6 times the recommended human dose based on AUC) in rats. No teratogenic effects were observed in rats at doses up to the maternally toxic dose of 200 mg/kg/day (approximately 2.7 times the recommended human dose based on AUC) or in rabbits at doses of up to 60 mg/kg/day (approximately 1.6 times the recommended human dose based on AUC), though fetal body weights were reduced at these doses.

8.2 Lactation

Risk Summary

There is no information regarding the presence of crizotinib or its metabolites in human milk, or the effects on the breastfed child or on milk production. Because of the potential for adverse reactions in breastfed children, advise women not to breastfeed during treatment with XALKORI and for 45 days after the last dose.

8.3 Females and Males of Reproductive Potential

Pregnancy Testing

Verify the pregnancy status of females of reproductive potential prior to initiating XALKORI [see Use in Specific Population (8.1)].

Contraception

XALKORI can cause fetal harm when administered to a pregnant woman [see Use in Specific Populations (8.1)].

Females

Advise females of reproductive potential to use effective contraception during treatment with XALKORI and for 45 days after the last dose.

Males

Because of the potential for genotoxicity, advise male patients with female partners of reproductive potential to use condoms during treatment with XALKORI and for 90 days after the last dose [see Nonclinical Toxicology (13.1)].

Infertility

Based on reproductive organ findings in animals, XALKORI may cause reduced fertility in females and males of reproductive potential. It is not known whether these effects on fertility are reversible [see Nonclinical Toxicology (13.1)].

8.4 Pediatric Use

The safety and effectiveness of XALKORI have been established in pediatric patients 1 year of age and older with relapsed or refractory, systemic ALK-positive ALCL or with unresectable, recurrent, or refractory ALK-positive IMT [see Adverse Reactions (6.1), Clinical Studies (14.2, 14.3)]. The safety and effectiveness have not been established in pediatric patients younger than 1 year of age with ALCL or with IMT, or in any pediatric patients with NSCLC.

In a study that evaluated XALKORI in combination with chemotherapy in pediatric patients with newly diagnosed ALCL (Study ANHL12P1; NCT01979536), 13 of 66 (20%) patients had a Grade 2 or higher thromboembolic event, including pulmonary embolism in 6%. The safety and effectiveness of XALKORI in combination with chemotherapy have not been established in patients with newly diagnosed ALCL.

Juvenile Animal Toxicity Data

Decreased bone formation in growing long bones was observed in immature rats at 150 mg/kg/day following once daily dosing for 28 days (approximately 5.4 times the recommended human dose based on AUC). Other toxicities of potential concern to pediatric patients have not been evaluated in juvenile animals.

8.5 Geriatric Use

Of the total number of patients with ALK-positive metastatic NSCLC in clinical studies of XALKORI (n=1669), 16% were 65 years or older and 3.8% were 75 years or older. No overall differences in safety or effectiveness were observed between these patients and younger patients.

Clinical studies of XALKORI in patients with ROS1-positive metastatic NSCLC did not include sufficient numbers of patients age 65 years and older to determine whether they respond differently from younger patients.

8.6 Hepatic Impairment

Crizotinib concentrations increased in patients with pre-existing moderate (any AST and total bilirubin greater than 1.5 times ULN and less than or equal to 3 times ULN) or severe (any AST and total bilirubin greater than 3 times ULN) hepatic impairment [see Clinical Pharmacology (12.3)]. Reduce XALKORI dosage in patients with moderate or severe hepatic impairment [see Dosage and Administration (2.7)]. No dose adjustment is recommended in patients with pre-existing mild hepatic impairment (AST > ULN and total bilirubin less than or equal to 1 times ULN or any AST and total bilirubin greater than 1 times ULN but less than or equal to1.5 times ULN).

8.7 Renal Impairment

Increased exposure to crizotinib occurred in patients with pre-existing severe renal impairment (CLcr less than 30 mL/min calculated using the modified Cockcroft-Gault equation for adult patients and the Schwartz equation for pediatric patients) not requiring dialysis, therefore reduce dosage of XALKORI in these patients [see Dosage and Administration (2.8), Clinical Pharmacology (12.3)]. No dose adjustment is recommended in patients with mild to moderate renal impairment (CLcr 30 to 89 mL/min).

11 DESCRIPTION

Crizotinib is a kinase inhibitor. The molecular formula for crizotinib is C21H22Cl2FN5O and the molecular weight is 450.34 daltons. Crizotinib is described chemically as (R)-3-[1-(2,6-Dichloro-3-fluorophenyl)ethoxy]-5-[1-(piperidin-4-yl)-1H-pyrazol-4-yl]pyridin-2-amine.

The chemical structure of crizotinib is shown below:

Crizotinib is a white to pale-yellow powder with a pKa of 9.4 (piperidinium cation) and 5.6 (pyridinium cation). The solubility of crizotinib in aqueous media decreases over the range pH 1.6 to pH 8.2 from greater than 10 mg/mL to less than 0.1 mg/mL. The log of the distribution coefficient (octanol/water) at pH 7.4 is 1.65.

Capsules:

XALKORI (crizotinib) capsules for oral administration are supplied as printed hard-shell capsules containing 250 mg or 200 mg of crizotinib together with colloidal silicon dioxide, microcrystalline cellulose, anhydrous dibasic calcium phosphate, sodium starch glycolate, magnesium stearate, and hard gelatin capsule shells as inactive ingredients.

The pink opaque capsule shell components contain gelatin, titanium dioxide, and red iron oxide. The white opaque capsule shell components contain gelatin and titanium dioxide. The printing ink contains shellac, propylene glycol, strong ammonia solution, potassium hydroxide, and black iron oxide.

Oral Pellets:

XALKORI (crizotinib) oral pellets for oral administration are supplied as 20 mg, 50 mg, 150 mg of crizotinib contained in hard gelatin capsules. The inactive ingredients in the uncoated pellets are poloxamer and stearyl alcohol. The film-coating consists of hypromellose, glyceryl monostearate, medium chain triglycerides, polyethylene glycol/macrogol, sucrose, and talc.

12 CLINICAL PHARMACOLOGY

12.1 Mechanism of Action

Crizotinib is an inhibitor of receptor tyrosine kinases including ALK, Hepatocyte Growth Factor Receptor (HGFR, c-Met), ROS1 (c-ros), and Recepteur d'Origine Nantais (RON). Translocations can affect the ALK gene resulting in the expression of oncogenic fusion proteins. The formation of ALK fusion proteins results in activation and dysregulation of the gene's expression and signaling which can contribute to increased cell proliferation and survival in tumors expressing these proteins. Crizotinib demonstrated concentration-dependent inhibition of ALK, ROS1, and c-Met phosphorylation in cell-based assays using tumor cell lines and demonstrated antitumor activity in mice bearing tumor xenografts that expressed echinoderm microtubule-associated protein-like 4 (EML4)- or nucleophosmin (NPM)-ALK fusion proteins or c-Met.

In vitro, crizotinib induced apoptosis and inhibited proliferation and ALK-mediated signaling in ALCL-derived cell lines (containing NPM-ALK) at clinically achievable exposures. In vivo data obtained in an ALCL-derived mouse model showed complete regression of the tumor at a dose of 100 mg/kg once daily.

12.2 Pharmacodynamics

Cardiac Electrophysiology

In an ECG substudy conducted in 52 patients with ALK-positive NSCLC, the maximum mean QTcF (corrected QT by the Fridericia method) change from baseline was 12.3 ms (2-sided 90% upper CI: 19.5 ms) following administration of XALKORI 250 mg orally twice daily. An exposure-QT analysis suggested a crizotinib plasma concentration-dependent increase in QTcF [see Warnings and Precautions (5.3)].

12.3 Pharmacokinetics

Following XALKORI 250 mg capsules twice daily, steady-state was reached within 15 days with a median accumulation ratio of 4.8. Steady-state minimum concentration (Cmin.ss) and AUC increased in a greater than dose-proportional manner over the dose range of 200 mg to 300 mg twice daily (0.8 to 1.2 times the approved recommended dosage).

Absorption

A single crizotinib capsule dose was absorbed with median time to achieve peak concentration (Tmax) of 4 to 6 hours, and the mean absolute bioavailability of 43% (range: 32% to 66%).

The oral pellets had a comparable crizotinib bioavailability compared with the capsules.

Effect of Food

A high-fat meal, reduced AUC0-INF and maximum plasma concentration (Cmax) of crizotinib each by 14% for the capsule formulation; reduced AUC0-INF and Cmax of crizotinib by 15% and 23%, respectively, for the pellet formulation as compared to those under fasted conditions.

Distribution

The geometric mean volume of distribution (Vss) of crizotinib was 1772 L following a single intravenous dose. Protein binding of crizotinib is 91% and is independent of drug concentration in vitro. Crizotinib is a substrate for P-glycoprotein (P-gp) in vitro. The blood-to-plasma concentration ratio is approximately 1.

Elimination

The mean apparent plasma terminal half-life of crizotinib was 42 hours following single doses of crizotinib in patients. The mean apparent clearance (CL/F) of crizotinib was lower at steady-state (60 L/h) after 250 mg twice daily than after a single 250 mg oral dose (100 L/h).

Metabolism

Crizotinib is predominantly metabolized by CYP3A.

Excretion

Following administration of a single oral 250 mg dose of radiolabeled crizotinib dose to healthy subjects, 63% (53% as unchanged) of the administered dose was recovered in feces and 22% (2.3% as unchanged) in urine.

Specific Populations

No clinically significant difference in crizotinib pharmacokinetics were observed based on age, sex, or ethnicity (Asian, non-Asian). For patients <18 years of age, body weight has a significant effect on the pharmacokinetics of crizotinib, with lower crizotinib exposures observed in patients with higher body weight.

Pediatric Patients

In pediatric patients, crizotinib steady-state exposure increased proportionally with dose over the dose range of 165 mg/m^2 to 280 mg/m^2 orally twice daily. At a dosing regimen of 280 mg/m^2 (approximately 2 times the recommended adult dose), geometric mean (CV%) steady-state maximum plasma concentrations (Cmax) of crizotinib was 621 (73%) ng/mL and AUC0–tau was 6530 (34%) ng∙hr/mL.

Patients with Hepatic Impairment

Steady-state mean crizotinib AUC and Cmax decreased by 9% in patients with mild hepatic impairment (AST >ULN and total bilirubin ≤1 times ULN or any AST and total bilirubin >1 times ULN but ≤1.5 times ULN) compared to patients with normal hepatic function following XALKORI 250 mg orally twice daily.

Steady-state mean crizotinib AUC increased by 14% and Cmax increased by 9% in patients with moderate hepatic impairment (any AST and total bilirubin >1.5 times ULN and ≤3 times ULN) following XALKORI 200 mg orally twice daily compared with patients with normal hepatic function following XALKORI 250 mg orally twice daily.

Mean crizotinib AUC decreased by 35% and Cmax decreased by 27% in patients with severe hepatic impairment (any AST and total bilirubin >3 times ULN) following XALKORI 250 mg orally once daily compared with patients with normal hepatic function following XALKORI 250 mg orally twice daily [see Dosage and Administration (2.7), Use in Specific Populations (8.6)].

Patients with Renal Impairment

Mild or moderate renal impairment (CLcr of 60–89 ml/min or 30–59 ml/min, respectively, calculated using the modified Cockcroft-Gault equation) has no clinically significant effect on the exposure of crizotinib. Following a single 250 mg dose, the mean AUC0–INF of crizotinib increased by 79% and the mean Cmax increased by 34% in patients with severe renal impairment (CLcr <30 mL/min) who did not require dialysis compared to those with normal renal function (CLcr ≥90 mL/min). Similar changes in AUC0–INF and Cmax were observed for the active metabolite of crizotinib [see Dosage and Administration (2.8), Use in Specific Populations (8.7)].

Drug Interaction Studies

Clinical Studies

Gastric Acid Reducing Agents: No clinically significant differences in crizotinib pharmacokinetics were observed when used concomitantly with esomeprazole, a proton pump inhibitor.

Strong CYP3A Inhibitors: Coadministration of a single 150 mg oral dose of crizotinib with ketoconazole, a strong CYP3A inhibitor, increased crizotinib AUC0–INF by 216% and Cmax by 44% compared to crizotinib alone. Coadministration of XALKORI 250 mg orally once daily with itraconazole, a strong CYP3A inhibitor, increased crizotinib steady-state AUC by 57% and Cmax by 33% compared to crizotinib alone [see Drug Interactions (7.1)].

Strong CYP3A Inducers: Coadministration of XALKORI 250 mg orally twice daily with rifampin, a strong CYP3A inducer, decreased crizotinib steady-state AUC0–Tau by 84% and Cmax by 79%, compared to crizotinib alone [see Drug Interactions (7.1)].

CYP3A Substrates: Coadministration of XALKORI 250 mg orally twice daily for 28 days increased AUC0–INF of oral midazolam (CYP3A substrate) 3.7-fold compared to midazolam alone [see Drug Interactions (7.2)].

In Vitro Studies

CYP Enzymes: Crizotinib inhibits CYP2B6 in vitro. Crizotinib does not inhibit CYP1A2, CYP2C8, CYP2C9, CYP2C19, or CYP2D6. Crizotinib does not induce CYP1A2, CYP2B6, CYP2C8, CYP2C9, CYP2C19, or CYP3A.

UDP-glucuronosyltransferase (UGT): Crizotinib does not inhibit UGT1A1, UGT1A4, UGT1A6, UGT1A9 or UGT2B7.

Transporters: Crizotinib inhibits P-gp, organic cation transporter (OCT) 1, and OCT2. Crizotinib does not inhibit organic anion transporting polypeptides (OATP) B1, OATP1B3, organic anion transporter (OAT) 1, OAT3, or bile salt export pump transporter (BSEP).

13 NONCLINICAL TOXICOLOGY

13.1 Carcinogenesis, Mutagenesis, Impairment of Fertility

Carcinogenicity studies with crizotinib have not been conducted.

Crizotinib was genotoxic in an in vitro micronucleus assay in Chinese Hamster Ovary cultures, in an in vitro human lymphocyte chromosome aberration assay, and in in vivo rat bone marrow micronucleus assays. Crizotinib was not mutagenic in vitro in the bacterial reverse mutation (Ames) assay.

No specific studies with crizotinib have been conducted in animals to evaluate the effect on fertility; however, crizotinib is considered to have the potential to impair reproductive function and fertility in humans based on findings in repeat-dose toxicity studies in the rat. Findings observed in the male reproductive tract included testicular pachytene spermatocyte degeneration in rats given greater than or equal to 50 mg/kg/day for 28 days (greater than 1.7 times the recommended human dose based on AUC). Findings observed in the female reproductive tract included single-cell necrosis of ovarian follicles of a rat given 500 mg/kg/day (approximately 10 times the recommended human dose based on body surface area) for 3 days.

14 CLINICAL STUDIES

14.1 ALK- or ROS1-Positive Metastatic Non-Small Cell Lung Cancer

Previously Untreated ALK-Positive Metastatic NSCLC - Study 1 (PROFILE 1014; NCT01154140)

The efficacy of XALKORI for the treatment of patients with ALK-positive metastatic NSCLC, who had not received previous systemic treatment for advanced disease, was demonstrated in a randomized, multicenter, open-label, active-controlled study (Study 1). Patients were required to have ALK-positive NSCLC as identified by the FDA-approved assay, Vysis ALK Break-Apart fluorescence in situ hybridization (FISH) Probe Kit, prior to randomization. The major efficacy outcome measure was progression-free survival (PFS) according to Response Evaluation Criteria in Solid Tumors (RECIST) version 1.1 as assessed by independent radiology review (IRR) committee. Additional efficacy outcome measures included objective response rate (ORR) as assessed by IRR, DOR, and overall survival (OS). Patient-reported lung cancer symptoms were assessed at baseline and periodically during treatment.

Patients were randomized to receive XALKORI (n=172) or chemotherapy (n=171). Randomization was stratified by Eastern Cooperative Oncology Group (ECOG) performance status (0–1, 2), race (Asian, non-Asian), and brain metastases (present, absent). Patients in the XALKORI arm received XALKORI 250 mg orally twice daily until documented disease progression, intolerance to therapy, or the investigator determined that the patient was no longer experiencing clinical benefit. Chemotherapy consisted of pemetrexed 500 mg/m^2 with cisplatin 75 mg/m^2 or carboplatin AUC of 5 or 6 mg×min/mL by intravenous infusion every 3 weeks for up to 6 cycles. Patients in the chemotherapy arm were not permitted to receive maintenance chemotherapy. At the time of documented disease progression, as per independent radiology review, patients randomized to chemotherapy were offered XALKORI.

The demographic characteristics of the overall study population were 62% female, median age of 53 years, baseline ECOG performance status 0 or 1 (95%), 51% White and 46% Asian, 4% current smokers, 32% past smokers, and 64% never smokers. The disease characteristics of the overall study population were metastatic disease in 98% of patients, 92% of patients' tumors were classified as adenocarcinoma histology, 27% of patients had brain metastases, and 7% received systemic chemotherapy as adjuvant or neoadjuvant therapy. At the time of the final analysis of overall survival, 84% of patients randomized to the chemotherapy arm subsequently received XALKORI.

Study 1 demonstrated a statistically significant improvement in PFS in patients treated with XALKORI. There was no statistically significant difference in OS between patients treated with XALKORI and patients treated with chemotherapy. Table 16 and Figure 1 summarize the efficacy results. Exploratory patient-reported symptom measures of baseline and post-treatment dyspnea, cough, and chest pain suggested a delay in time to development of or worsening of dyspnea, but not cough or chest pain, in patients treated with XALKORI as compared to chemotherapy. The patient-reported delay in onset or worsening of dyspnea may be an overestimation because patients were not blinded to treatment assignment.

Table 16. Previously Untreated ALK-Positive Metastatic NSCLC - Efficacy Results in Study 1
 | XALKORI (N=172) | Chemotherapy (N=171)
Progression-Free Survival (Based on IRR)
Number of Events (%) | 100 (58%) | 137 (80%)
Progressive Disease | 89 (52%) | 132 (77%)
Death | 11 (6%) | 5 (3%)
Median, Months (95% CI) | 10.9 (8.3, 13.9) | 7.0 (6.8, 8.2)
HR (95% CI) [Based on the Cox proportional hazards stratified analysis.] | 0.45 (0.35, 0.60)
p-value [Based on the stratified log-rank test.] | <0.001
Overall Survival
Number of Events (%) | 71 (41%) | 81 (47%)
Median, Months (95% CI) | NR (45.8, NR) | 47.5 (32.2, NR)
HR (95% CI) | 0.76 (0.55, 1.05)
p-value | 0.098
Tumor Responses (Based on IRR)
Objective Response Rate % (95% CI) | 74% (67, 81) | 45% (37, 53)
CR, n (%) | 3 (1.7%) | 2 (1.2%)
PR, n (%) | 125 (73%) | 75 (44%)
p-value [Based on the stratified Cochran-Mantel-Haenszel test.] | <0.001
Duration of Response
Median, Months (95% CI) | 11.3 (8.1, 13.8) | 5.3 (4.1, 5.8)
HR=hazard ratio; CI=confidence interval; IRR=independent radiology review; NR=not reached; CR=complete response; PR=partial response.

Figure 1. Kaplan-Meier Curves of Progression-Free Survival as Assessed by IRR in Study 1

Previously Treated ALK-Positive Metastatic NSCLC - Study 2 (PROFILE 1007; NCT00932893)

The efficacy of XALKORI as monotherapy for the treatment of 347 patients with ALK-positive metastatic NSCLC, previously treated with 1 platinum-based chemotherapy regimen, were demonstrated in a randomized, multicenter, open-label, active-controlled study (Study 2). The major efficacy outcome was PFS according to RECIST version 1.1 as assessed by IRR. Additional efficacy outcomes included ORR as assessed by IRR, DOR, and OS.

Patients were randomized to receive XALKORI 250 mg orally twice daily (n=173) or chemotherapy (n=174). Chemotherapy consisted of pemetrexed 500 mg/m^2 (if pemetrexed-naïve; n=99) or docetaxel 75 mg/m^2 (n=72) intravenously (IV) every 21 days. Patients in both treatment arms continued treatment until documented disease progression, intolerance to therapy, or the investigator determined that the patient was no longer experiencing clinical benefit. Randomization was stratified by ECOG performance status (0–1, 2), brain metastases (present, absent), and prior EGFR tyrosine kinase inhibitor treatment (yes, no). Patients were required to have ALK-positive NSCLC as identified by the FDA-approved assay, Vysis ALK Break-Apart FISH Probe Kit, prior to randomization.

The demographic characteristics of the overall study population were 56% female, median age of 50 years, baseline ECOG performance status 0 or 1 (90%), 52% White and 45% Asian, 4% current smokers, 33% past smokers, and 63% never smokers. The disease characteristics of the overall study population were metastatic disease in at least 95% of patients and at least 93% of patients' tumors were classified as adenocarcinoma histology. At the time of the final analysis of overall survival, 89% of patients randomized to the chemotherapy arm subsequently received XALKORI.

Study 2 demonstrated a statistically significant improvement in PFS in the patients treated with XALKORI. Table 17 and Figure 2 summarize the efficacy results.

Table 17. Previously Treated ALK-Positive Metastatic NSCLC - Efficacy Results in Study 2
 | XALKORI (N=173) | Chemotherapy (N=174)
Progression-Free Survival (Based on IRR)
Number of Events (%) | 100 (58%) | 127 (73%)
Progressive Disease | 84 (49%) | 119 (68%)
Death | 16 (9%) | 8 (5%)
Median, Months (95% CI) | 7.7 (6.0, 8.8) | 3.0 [For pemetrexed, the median PFS was 4.2 months. For docetaxel, the median PFS was 2.6 months.] (2.6, 4.3)
HR (95% CI) [Based on the Cox proportional hazards stratified analysis.] | 0.49 (0.37, 0.64)
p-value [Based on the stratified log-rank test.] | <0.001
Overall Survival
Number of Events (%) | 116 (67%) | 126 (72%)
Median, Months (95% CI) | 21.7 (18.9,30.5) | 21.9 (16.8,26.0)
HR (95% CI) | 0.85 (0.66, 1.10)
p-value | 0.229
Tumor Responses (Based on IRR)
Objective Response Rate % (95% CI) | 65% (58, 72) | 20% (14, 26)
CR, n (%) | 1 (0.6%) | 0
PR, n (%) | 112 (65%) | 34 (20%)
p-value [Based on the stratified Cochran-Mantel-Haenszel test.] | <0.001
Duration of Response
Median, Months (95% CI) | 7.4 (6.1, 9.7) | 5.6 (3.4, 8.3)
HR=hazard ratio; CI=confidence interval; IRR=independent radiology review; CR=complete response; PR=partial response.

Figure 2. Kaplan-Meier Curves of Progression-Free Survival as Assessed by IRR in Study 2

ROS1-Positive Metastatic NSCLC - Study 3 (PROFILE 1001; NCT00585195)

The efficacy and safety of XALKORI was investigated in a multicenter, single-arm study (Study 3), in which patients with ROS1-positive metastatic NSCLC received XALKORI 250 mg orally twice daily. Patients were required to have histologically-confirmed advanced NSCLC with a ROS1 rearrangement, age 18 years or older, ECOG performance status of 0, 1, or 2, and measurable disease. The efficacy outcome measures were ORR and DOR according to RECIST version 1.0 as assessed by IRR and investigator, with imaging performed every 8 weeks for the first 60 weeks.

Baseline demographic and disease characteristics were female (56%), median age of 53 years, baseline ECOG performance status of 0 or 1 (98%), White (54%), Asian (42%), past smokers (22%), never smokers (78%), metastatic disease (92%), adenocarcinoma (96%), no prior systemic therapy for metastatic disease (14%), and prior platinum-based chemotherapy for metastatic disease (80%). The ROS1 status of NSCLC tissue samples was determined by laboratory-developed break-apart FISH (96%) or RT-PCR (4%) clinical trial assays. For assessment by FISH, ROS1 positivity required that ≥15% of a minimum of 50 evaluated nuclei contained a ROS1 gene rearrangement.

Efficacy results are summarized in Table 18.

Table 18. ROS1-Positive Metastatic NSCLC - Results [As assessed by RECIST version 1.0.] in Study 3
Efficacy Parameters | IRR (N=50) | Investigator-Assessed (N=50)
Objective Response Rate (95% CI) | 66% (51, 79) | 72% (58, 84)
Complete Response, n | 1 | 5
Partial Response, n | 32 | 31
Duration of Response
Median, Months (95% CI) | 18.3 (12.7, NR) | NR (14.5, NR)
IRR=independent radiology review; CI=confidence interval; NR=not reached.

14.2 Relapsed or Refractory, Systemic ALK-Positive Anaplastic Large Cell Lymphoma

The efficacy of XALKORI was evaluated in Study ADVL0912 (NCT00939770), a multicenter, single arm, open-label study in patients 1 to ≤21 years of age that included 26 patients with relapsed or refractory, systemic ALK-positive ALCL after at least one systemic treatment. ALK-positive status (confirmation of an ALK fusion) was determined locally by immunohistochemistry or fluorescence in situ hybridization. The study excluded patients with primary cutaneous ALCL or central nervous system involvement by lymphoma.

Patients received XALKORI 280 mg/m^2 (20 patients) or 165 mg/m^2 (6 patients) orally twice daily until disease progression or unacceptable toxicity. Patients were permitted to discontinue XALKORI to undergo hematopoietic stem cell transplantation (HSCT).

Of the 26 patients evaluated, the median age was 11 years (range: 3 to 20); 69% were male, 54% were White, 19% Black, 8% Asian. Patient enrollment by age category was 4 patients from 3 to <6 years, 11 patients from 6 to <12 years, 7 patients from 12 to <18 years, and 4 patients from 18 to ≤21 years.

All patients had received multi-agent systemic therapy, 2 (8%) had received a prior HSCT and 4 (15%) had received at least 3 prior therapies.

Efficacy was based on objective response rate and duration of response, as assessed by an independent review committee (Table 19). The median time to first response was 3.9 weeks (range: 3.5 to 9.1 weeks).

Table 19. Efficacy in Relapsed or Refractory, Systemic ALK-Positive ALCL
Efficacy Parameter | N=26
Objective response rate (95% CI, %) [Based on Lugano Classification.] , [95% CI based on Wilson score method.] | 88% (71, 96)
Complete response, n | 21 (81%)
Partial response, n | 2 (8%)
Duration of response [Of 23 patients with objective response, 2 had disease progression and the remainder (91% of responding patients) were censored.]
Patients maintaining response at 3 months, n/N | 13/23 (57%)
Patients maintaining response at 6 months, n/N | 9/23 (39%)
Patients maintaining response at 12 months, n/N | 5/23 (22%)
CI=confidence interval; N/n=number of patients

14.3 Unresectable, Recurrent, or Refractory ALK-Positive Inflammatory Myofibroblastic Tumor

Pediatric Patients with ALK-positive IMT

Study ADVL0912

The efficacy of XALKORI was evaluated in Study ADVL0912 (NCT00939770), a multicenter, single-arm, open-label study in patients 1 to ≤21 years of age that included 14 pediatric patients with unresectable, recurrent, or refractory ALK-positive IMT. Patients were required to have an ALK fusion determined locally by immunohistochemistry or fluorescence in situ hybridization. Patients (n=12) received XALKORI 280 mg/m^2 twice daily until disease progression or unacceptable toxicity. Two patients received a lower dose.

The demographic characteristics were median age 6.5 years (range: 2 to 13); 64% female; 71% White; 7% Black, 21% unknown; 21% Hispanic; and 71% had a Lansky/Karnofsky Score of 100. Patient enrollment by age was 4 patients from 2 to <6 years, 8 patients from 6 to <12 years, and 2 patients from 12 to <18 years.

A total of 12 (86%) patients received prior therapy. The most common prior therapy was surgery (57%).

The major efficacy outcome was objective response rate according to RECIST version 1.0 as assessed by an independent review committee (Table 20).

Table 20. Efficacy in Pediatric Patients with Unresectable, Recurrent, or Relapsed ALK-Positive IMT
Efficacy Parameter | N=14
Objective response rate (95% CI, %) [95% CI based on Clopper–Pearson exact method.] | 86% (57, 98)
Complete response, n (%) | 5 (36)
Partial response n (%) | 7 (50)
Duration of response [Estimated using descriptive statistics.] | N=12
≥6 months, n (%) | 7 (58)
≥12 months, n (%) | 7 (58)
CI=confidence interval; N/n=number of patients.

Adult Patients with ALK-positive IMT

Study A8081013

The efficacy of XALKORI was evaluated in Study A8081013 (NCT01121588), a multicenter, single-arm, open-label study that included 7 adult patients with unresectable, recurrent, or refractory ALK-positive IMT. ALK fusion was determined locally by immunohistochemistry or fluorescence in situ hybridization. Patients received XALKORI 250 mg twice daily.

The demographic characteristics were median age 38 years (range: 23 to 73); 57% male; 57% White, 43% Asian; and 86% ECOG performance status of 0 or 1. Two (29%) patients had at least one prior systemic treatment.

The major efficacy outcome was objective response rate according to RECIST version 1.1 per investigator assessment. For the 7 patients with ALK-positive IMT, 5 experienced a response including 1 complete response. The DOR was ≥6 months for all 5 patients and ≥12 months for 2 patients.

16 HOW SUPPLIED/STORAGE AND HANDLING

Capsules:

- 200 mg capsules
  Hard gelatin capsule with pink opaque cap and white opaque body, printed with black ink "Pfizer" on the cap, "CRZ 200" on the body; available in:
  Bottles of 60 capsules: NDC 0069-8141-20
- 250 mg capsules
  Hard gelatin capsule with pink opaque cap and body, printed with black ink "Pfizer" on the cap, "CRZ 250" on the body; available in:
  Bottles of 60 capsules: NDC 0069-8140-20

Store at room temperature 20° to 25°C (68° to 77°F); excursions permitted between 15° to 30°C (59° to 86°F) [see USP Controlled Room Temperature].

Oral Pellets:

- 20 mg oral pellets
  Hard gelatin capsule, size 4, light blue opaque cap and white opaque body, printed with black ink “Pfizer” on the cap, “CRZ 20” on the body; available in:
  Bottles of 60 capsules: NDC 0069-0251-60
- 50 mg oral pellets
  Hard gelatin capsule, size 3, gray opaque cap and light gray opaque body, printed with black ink “Pfizer” on the cap, “CRZ 50” on the body; available in:
  Bottles of 60 capsules: NDC 0069-0507-60
- 150 mg oral pellets
  Hard gelatin capsule, size 0, light blue opaque cap and body, printed with black ink “Pfizer” on the cap, “CRZ 150” on the body; available in:
  Bottles of 60 capsules: NDC 0069-1500-60

Store at 20°C to 25°C (68°F to 77°F); excursions permitted between 15°C to 30°C (59°F to 86°F) [see USP Controlled Room Temperature].

17 PATIENT COUNSELING INFORMATION

Advise the patient or caregiver to read the FDA-approved patient labeling (Medication Guide; Instructions for Use).

Hepatotoxicity

Inform patients to immediately report symptoms of hepatotoxicity [see Warnings and Precautions (5.1)].

Interstitial Lung Disease (Pneumonitis)

Advise patients to immediately report any new or worsening pulmonary symptoms [see Warnings and Precautions (5.2)].

Bradycardia

Advise patients to report any symptoms of bradycardia and to inform their healthcare provider about the use of any heart or blood pressure medications [see Warnings and Precautions (5.4)].

Severe Visual Loss

Inform patients of the potential risk of severe visual loss and to immediately contact their healthcare provider if they develop severe visual loss. Inform patients that visual changes such as perceived flashes of light, blurry vision, light sensitivity, and floaters are commonly reported adverse reactions and may occur while driving or operating machinery. The onset of visual disorders most commonly occurs during the first week of treatment [see Warnings and Precautions (5.5), Adverse Reactions (6)].

Gastrointestinal Toxicity in Pediatric and Young Adult Patients with ALCL or Pediatric Patients with IMT

Inform patients with ALCL or pediatric patients with IMT of the risk of severe nausea, vomiting, diarrhea, and stomatitis. Advise patients to immediately inform their healthcare provider of problems with swallowing, vomiting, or diarrhea [see Warnings and Precautions (5.6)].

Drug Interactions

Inform patients to avoid grapefruit or grapefruit juice while taking XALKORI. Advise patients to inform their healthcare providers of all concomitant medications, including prescription medicines, over-the-counter drugs, vitamins, and herbal products [see Drug Interactions (7)].

Photosensitivity

Inform patients of the signs and symptoms of photosensitivity. Advise patients to avoid prolonged sun exposure and to use sunscreen or protective clothing during treatment with XALKORI [see Adverse Reactions (6.1)].

Dosage and Administration

Advise patients to take XALKORI with or without food. If a patient misses a dose, advise the patient to take it as soon as remembered unless it is less than 6 hours until the next dose, in which case, advise the patient not to take the missed dose. If a patient vomits after taking a dose of XALKORI, advise the patient not to take an extra dose, but to take the next dose at the regular time [see Dosage and Administration (2.4)].

Capsules:

Advise patients to swallow XALKORI capsules whole [see Dosage and Administration (2.4)].

Oral Pellets:

Inform patient or caregiver to open the encapsulated XALKORI oral pellets and administer the oral pellets directly in the patient’s mouth or with a consumer-supplied oral dosing aid, for example a spoon or medicine cup. Advise patient or caregiver that the oral pellets are not to be chewed and to give a sufficient amount of water after pellets are administered to ensure all oral pellets are swallowed [see Dosage and Administration (2.4)].

Embryo-Fetal Toxicity

Advise females of reproductive potential of the potential risk to a fetus and to inform their healthcare provider of a known or suspected pregnancy [see Warnings and Precautions (5.7), Use in Specific Populations (8.1)].

Females and Males of Reproductive Potential

Advise females of reproductive potential to use effective contraception during treatment with XALKORI and for 45 days after the last dose [see Use in Specific Populations (8.3)].

Advise male patients with female partners of reproductive potential to use condoms during treatment with XALKORI and for 90 days after the last dose [see Use in Specific Populations (8.3), Nonclinical Toxicology (13.1)].

Lactation

Advise females not to breastfeed during treatment with XALKORI and for 45 days after the last dose [see Use in Specific Populations (8.2)].

Infertility

Advise females and males of reproductive potential of the potential for reduced fertility from XALKORI [see Use in Specific Populations (8.3), Nonclinical Toxicology (13.1)].

This product's labeling may have been updated. For the most recent prescribing information, please visit www.Pfizer.com. For medical information about XALKORI, please visit www.pfizermedinfo.com or call 1-800-438-1985.

LAB-0440-28.0

MEDICATION GUIDE

XALKORI® (zal-KOR-ee)
(crizotinib)
capsules

XALKORI® (zal-KOR-ee)
(crizotinib)
oral pellets

What is the most important information I should know about XALKORI?
XALKORI may cause serious side effects, including:

- Liver problems. XALKORI may cause life-threatening liver injury that may lead to death. Your healthcare provider should do blood tests to check your liver every 2 weeks during the first 2 months of treatment with XALKORI, then 1 time a month and as recommended by your healthcare provider during treatment. Tell your healthcare provider right away if you develop any of the following new or worsening symptoms:

- yellowing of your skin or the white part of your eyes
- severe tiredness
- dark or brown (tea color) urine
- nausea or vomiting

- decreased appetite
- pain on the right side of your stomach
- bleed or bruise more easily than normal
- itching

- Lung problems (pneumonitis). XALKORI may cause life-threatening lung problems that may lead to death. Symptoms may be similar to those symptoms from lung cancer. Tell your healthcare provider right away if you have any new or worsening symptoms, including:
  - trouble breathing or shortness of breath
  - cough with or without mucous
  - fever
- Heart problems. XALKORI may cause very slow, very fast, or abnormal heartbeats. Your healthcare provider may check your pulse rate and blood pressure regularly during treatment with XALKORI. Tell your healthcare provider right away if you feel dizzy or faint or have abnormal heartbeats. Tell your healthcare provider if you take any heart or blood pressure medicines.
- Severe vision problems. Vision problems are common with XALKORI. These problems usually happen within 1 week of starting treatment with XALKORI. Vision problems with XALKORI can be severe and may cause partial or complete loss of vision in one or both eyes. Your healthcare provider may hold or permanently stop your treatment with XALKORI and refer you to an eye specialist if any vision problems develop during treatment with XALKORI. Tell your healthcare provider right away if you have any new vision problems, loss of vision or any change in vision, including:

- double vision
- seeing flashes of light
- blurry vision

- light hurting your eyes
- new or increased floaters

In addition, for children or young adults taking XALKORI to treat anaplastic large cell lymphoma (ALCL) or children taking XALKORI to treat inflammatory myofibroblastic tumor (IMT):
Your healthcare provider may refer you to an eye specialist before starting XALKORI, and within 1 month of starting XALKORI to check for vision problems. You should have an eye examination every 3 months during treatment with XALKORI and more often if there are any new vision problems.

- Severe stomach, intestine, and mouth (gastrointestinal) problems in children or young adults with ALCL or children with IMT. XALKORI may cause severe diarrhea, nausea, vomiting, or mouth sores. Tell your healthcare provider right away if problems with swallowing, vomiting, or diarrhea develop during treatment with XALKORI.
  - Your healthcare provider may give medicines as needed to prevent or treat diarrhea, nausea, and vomiting.
  - Your healthcare provider may recommend drinking more fluids or may prescribe electrolyte supplements or other kinds of nutritional support if severe symptoms develop.

See "What are possible side effects of XALKORI?" for more information about side effects.

What is XALKORI?
XALKORI is a prescription medicine that is used to treat:

- adults with non-small cell lung cancer (NSCLC) that has spread to other parts of the body and is caused by a defect in either a gene called ALK (anaplastic lymphoma kinase) or a gene called ROS1.
- children 1 year of age and older and young adults with ALCL when your ALCL with a defect in a gene called ALK has returned or you have tried a treatment and it did not work or is no longer working.
  - It is not known if XALKORI is safe and effective in older adults with ALCL.
- adults and children 1 year of age and older with IMT when your IMT with a defect in a gene called ALK cannot be removed by surgery, has returned, or you have tried a treatment and it did not work or is no longer working.

It is not known if XALKORI is safe and effective in children younger than 1 year of age with ALCL or IMT, or in any children with NSCLC.

Before taking XALKORI, tell your healthcare provider about all of your medical conditions, including if you:

- have liver or kidney problems
- have lung problems
- have heart problems, including a condition called long QT syndrome
- have vision or eye problems
- are pregnant or plan to become pregnant. XALKORI can harm your unborn baby.
  Females who are able to become pregnant:
  - Your healthcare provider will check to see if you are pregnant before starting treatment with XALKORI.
  - Effective birth control (contraception) should be used during treatment with XALKORI and for 45 days after the last dose of XALKORI.
  - Tell your healthcare provider right away if you become pregnant or think you might be pregnant during treatment with XALKORI.
Males who have female partners who can become pregnant:
  1. You should use condoms during treatment with XALKORI and for 90 days after the last dose of XALKORI.
- are breastfeeding or plan to breastfeed. It is not known if XALKORI passes into your breast milk. Do not breastfeed during treatment with XALKORI and for 45 days after the last dose. Talk to your healthcare provider about the best way to feed your baby during this time.

Tell your healthcare provider about the medicines you take, including prescription and over-the-counter medicines, vitamins, and herbal supplements. XALKORI can affect the way other medicines work, and other medicines can affect how XALKORI works.

How should I take XALKORI?

- Take XALKORI exactly as prescribed by your healthcare provider.

XALKORI comes as capsules and oral pellets.

- If your healthcare provider prescribes XALKORI capsules:
  - Swallow XALKORI capsules whole. Do not chew, crush or split XALKORI capsules.
  - Take XALKORI capsules with or without food.
- If your healthcare provider prescribes XALKORI oral pellets:
  - See the Instructions for Use at the end of this Medication Guide for instructions about the right way to prepare and give or take XALKORI oral pellets.
  - XALKORI oral pellets should be poured from the shell(s) directly into the mouth, or given or taken with a spoon or medicine cup. Right after giving or taking the oral pellets, give or drink enough water to make sure all oral pellets are swallowed.
  - Do not swallow shells containing XALKORI oral pellets.
  - Do not chew or crush the XALKORI oral pellets.
  - Take XALKORI oral pellets with or without food.
- Your healthcare provider will check your blood cell counts weekly during the first month of treatment with XALKORI and then at least monthly during treatment.
- Your healthcare provider may change your dose, temporarily stop, or permanently stop treatment with XALKORI if you have certain side effects. Do not change the dose or stop treatment with XALKORI unless your healthcare provider tells you to.
- If a dose of XALKORI is missed, it should be taken as soon as you remember. If it is close to the time of the next dose (within 6 hours), the missed dose should be skipped, and the next dose should be taken at the regular time.
- If you vomit after taking a dose of XALKORI, do not take an extra dose. The next dose should be taken at the regular time.
- XALKORI should be given to children under adult supervision.

What should I avoid while taking XALKORI?

- Do not drink grapefruit juice, eat grapefruit or take supplements containing grapefruit extract during treatment with XALKORI. These may increase the amount of XALKORI in the blood.
- XALKORI can cause changes in vision, dizziness, and tiredness. Do not drive or operate machinery if you have any of these symptoms.
- Avoid spending prolonged time in sunlight. XALKORI can make your skin sensitive to the sun (photosensitivity), and you may burn more easily. You should use sunscreen and wear protective clothing that covers your skin to help protect against sunburn if you have to be in the sunlight during treatment with XALKORI.

What are the possible side effects of XALKORI?
XALKORI may cause serious side effects, including:

- See "What is the most important information I should know about XALKORI?"

The most common side effects of XALKORI in adults with NSCLC include:

- vision problems
- nausea, diarrhea, or vomiting
- swelling of your hands, feet, face, or eyes
- constipation
- increased liver function blood tests

- tiredness
- decreased appetite
- upper respiratory infection
- dizziness
- feeling of numbness or tingling in your arms or legs

The most common side effects of XALKORI in people with ALCL include:

- diarrhea, vomiting, or nausea
- vision problems
- headache
- muscle and joint pain
- mouth sores
- tiredness

- decreased appetite
- fever
- stomach-area (abdominal) pain
- cough
- itchy skin
- low blood counts

The most common side effects of XALKORI in adults with IMT include:

- vision problems
- nausea
- swelling of your hands, feet, face, or eyes

The most common side effects of XALKORI in children with IMT include:

- vomiting, nausea, or diarrhea
- stomach-area (abdominal) pain
- rash
- vision problems
- upper respiratory infection
- cough

- fever
- muscle and joint pain
- tiredness
- swelling of your hands, feet, face, or eyes
- constipation
- headache

XALKORI may cause fertility problems in females and males, which may affect the ability to have children. Talk to your healthcare provider if you have concerns about fertility.
These are not all of the possible side effects of XALKORI. Call your doctor for medical advice about side effects. You may report side effects to FDA at 1-800-FDA-1088.

How should I store XALKORI?

- Store XALKORI capsules at room temperature between 68°F to 77°F (20°C to 25°C).
- Store XALKORI oral pellets at room temperature between 68°F to 77°F (20°C to 25°C).

Keep XALKORI and all medicines out of the reach of children.

General information about the safe and effective use of XALKORI.
Medicines are sometimes prescribed for purposes other than those listed in a Medication Guide. Do not use XALKORI for a condition for which it was not prescribed. Do not give XALKORI to other people, even if they have the same symptoms that you have. It may harm them. You can ask your healthcare provider or pharmacist for more information about XALKORI that is written for health professionals.

What are the ingredients in XALKORI?
Active ingredient: crizotinib
Capsules inactive ingredients: colloidal silicon dioxide, microcrystalline cellulose, anhydrous dibasic calcium phosphate, sodium starch glycolate, magnesium stearate, and hard gelatin capsule shells.
Pink opaque capsule shell contains: gelatin, titanium dioxide, and red iron oxide.
White opaque capsule shell contains: gelatin and titanium dioxide.
Printing ink contains: shellac, propylene glycol, strong ammonia solution, potassium hydroxide, and black iron oxide.
Oral pellets inactive ingredients: The uncoated pellets contain poloxamer and stearyl alcohol. The film-coating contains hypromellose, glyceryl monostearate, medium chain triglycerides, polyethylene glycol/macrogol, sucrose, and talc.

LAB-0441-12.0
For more information, go to www.Pfizer.com or call 1-800-438-1985.

This Medication Guide has been approved by the U.S. Food and Drug Administration. Revised: Sep 2023

Instructions for Use

XALKORI® [zal-KOR-ee]

(crizotinib)

oral pellets

This Instructions for Use contains information on how to give or take XALKORI oral pellets. Read this Instructions for Use each time you get a refill. There may be new information. This information does not take the place of talking to your healthcare provider or pharmacist about your or your child’s medical condition or treatment.

Important information you need to know before giving or taking XALKORI oral pellets:

- XALKORI oral pellets come in a capsule “shell” that must be opened before giving or taking a dose. Do not swallow the shell containing the oral pellets. Do not chew or crush the oral pellets.
- XALKORI oral pellets come in 3 dosage strengths: 20 mg, 50 mg, and 150 mg. Your healthcare provider may combine different strengths for your prescribed dose. No more than 4 XALKORI oral pellet shells are to be used for a single dose.
- Your healthcare provider will decide the right dose of XALKORI oral pellets for you or your child. Follow your healthcare provider’s instructions for the dose of XALKORI oral pellets to give your child or for you to take.
- Empty XALKORI oral pellets from the shells as described in Steps 1 to 4 below.
- Check the expiration date on the bottle containing XALKORI oral pellets. Do not use XALKORI oral pellets after the expiration date on the bottle has passed.
- Ask your healthcare provider or pharmacist if you are not sure how to prepare and give or take the prescribed dose of XALKORI oral pellets.

Supplies needed to give or take XALKORI oral pellets:

- XALKORI oral pellet(s), as prescribed by your healthcare provider.
- Spoon or medicine cup (optional). See Step 4 “Giving or taking XALKORI oral pellets”.

Preparing XALKORI oral pellets (Steps 1 to 3):

Step 1 | Remove the number of XALKORI oral pellet shell(s) needed for the prescribed dose from each bottle(s).
Step 2 | - Hold the shell with the writing “Pfizer” at the top (see Figure A). - Tap the shell to make sure the oral pellets fall to the bottom. Gently squeeze the bottom of the shell to loosen the top of the shell from the bottom.
Step 2 | Figure A
Step 3 | Carefully hold and twist the top and bottom parts of the shell in opposite directions and pull apart to open the shell (see Figure B).; Figure B

Giving or taking XALKORI oral pellets (Step 4): There are 2 options for giving or taking the oral pellets.

Step 4 | Option 1; (Pour directly into the mouth) | - Pour all oral pellets from 1 shell directly into your or your child’s mouth (see Figure C). - Gently tap the shell body with a finger as needed to make sure all pellets come out. - Right after giving or taking XALKORI oral pellets, give or drink enough water to make sure all oral pellets are swallowed. - If more than 1 shell is required for the prescribed dose, repeat Steps 1 to 4 for giving or taking the oral pellets from each shell.
Step 4 | Option 1; (Pour directly into the mouth) | Figure C
Step 4 | Option 2; (Pour from a spoon or medicine cup) | - Empty the oral pellets from the shell(s) that make up the prescribed dose into a dry spoon or medicine cup (see Figure D). - Pour the oral pellets from the dry spoon or medicine cup into your or your child’s mouth. - Right after giving or taking XALKORI oral pellets, give or drink enough water to make sure all oral pellets are swallowed. - If the entire prescribed dose cannot be taken at one time, give or take the oral pellets in smaller portions followed by giving or drinking water until the entire prescribed dose is given or taken.
Step 4 | Option 2; (Pour from a spoon or medicine cup) | Figure D
After Step 4 is completed, other drinks or foods can be given or taken, except grapefruit juice, grapefruit, or supplements containing grapefruit extract.

Storing XALKORI oral pellets:

- Store XALKORI oral pellets at room temperature between 68°F to 77°F (20°C to 25°C).
- Keep XALKORI oral pellets and all medicines out of the reach of children.

Disposing of empty XALKORI oral pellet shells:

- Dispose of (throw away) the empty XALKORI oral pellet shell(s) in the household trash.
- Ask your pharmacist how to throw away medicines you no longer use or are expired.

For more information, go to www.Pfizer.com or call 1-800-438-1985.

LAB-1526-1.0

This Instructions for Use has been approved by the U.S. Food and Drug Administration.

Issued: 09/2023

PRINCIPAL DISPLAY PANEL - 250 mg Capsule Bottle Label

ALWAYS DISPENSE ENCLOSED MEDICATION
GUIDE TO EACH PATIENT

Pfizer
NDC 0069-8140-20

XALKORI®
(crizotinib) capsules
250 mg

Swallow capsule whole

60 Capsules
Rx only

PRINCIPAL DISPLAY PANEL - 200 mg Capsule Bottle Label

ALWAYS DISPENSE ENCLOSED MEDICATION
GUIDE TO EACH PATIENT

Pfizer
NDC 0069-8141-20

XALKORI®
(crizotinib) capsules
200 mg

Swallow capsule whole

60 Capsules
Rx only

PRINCIPAL DISPLAY PANEL - 20 mg Oral Pellets Label

ALWAYS DISPENSE ENCLOSED MEDICATION
GUIDE TO EACH PATIENT

NDC 0069-0251-60
Pfizer

XALKORI®
(crizotinib) oral pellets
20 mg

Open capsule shell to administer pellets.
Do not swallow capsule whole.
Do not crush or chew pellets.

60 Capsules
Rx only

PRINCIPAL DISPLAY PANEL - 50 mg Oral Pellets Label

ALWAYS DISPENSE ENCLOSED MEDICATION
GUIDE TO EACH PATIENT

NDC 0069-0507-60
Pfizer

XALKORI®
(crizotinib) oral pellets
50 mg

Open capsule shell to administer pellets.
Do not swallow capsule whole.
Do not crush or chew pellets.

60 Capsules
Rx only

PRINCIPAL DISPLAY PANEL - 150 mg Oral Pellets Label

ALWAYS DISPENSE ENCLOSED MEDICATION
GUIDE TO EACH PATIENT

NDC 0069-1500-60
Pfizer

XALKORI®
(crizotinib) oral pellets
150 mg

Open capsule shell to administer pellets.
Do not swallow capsule whole.
Do not crush or chew pellets.

60 Capsules
Rx only